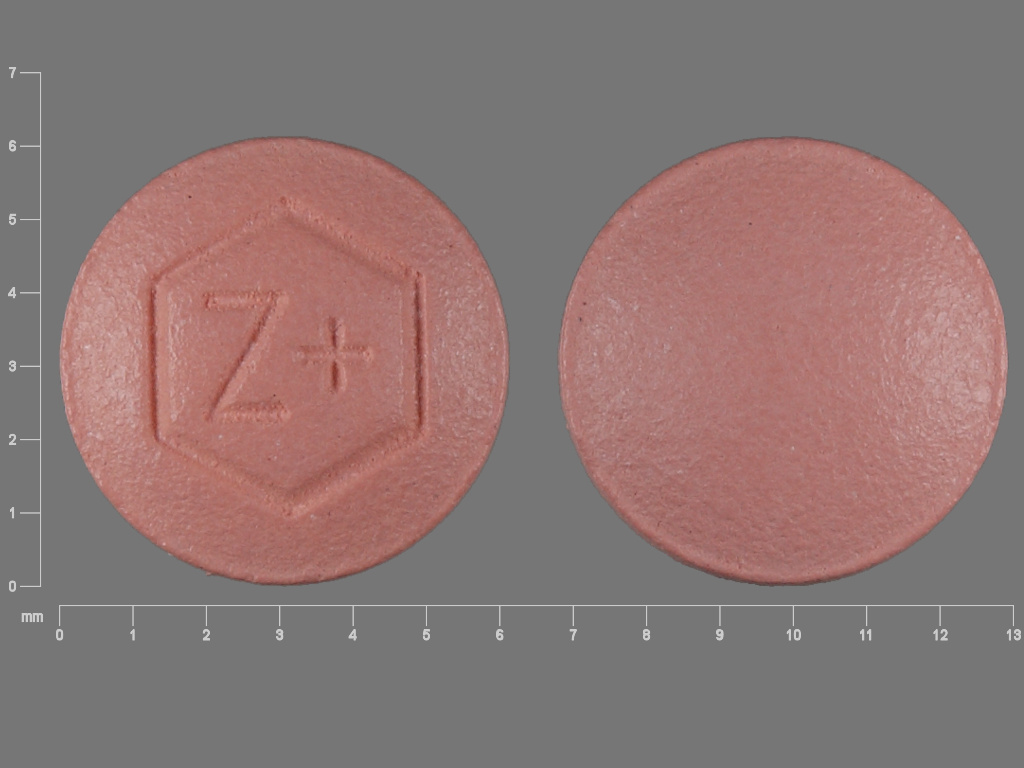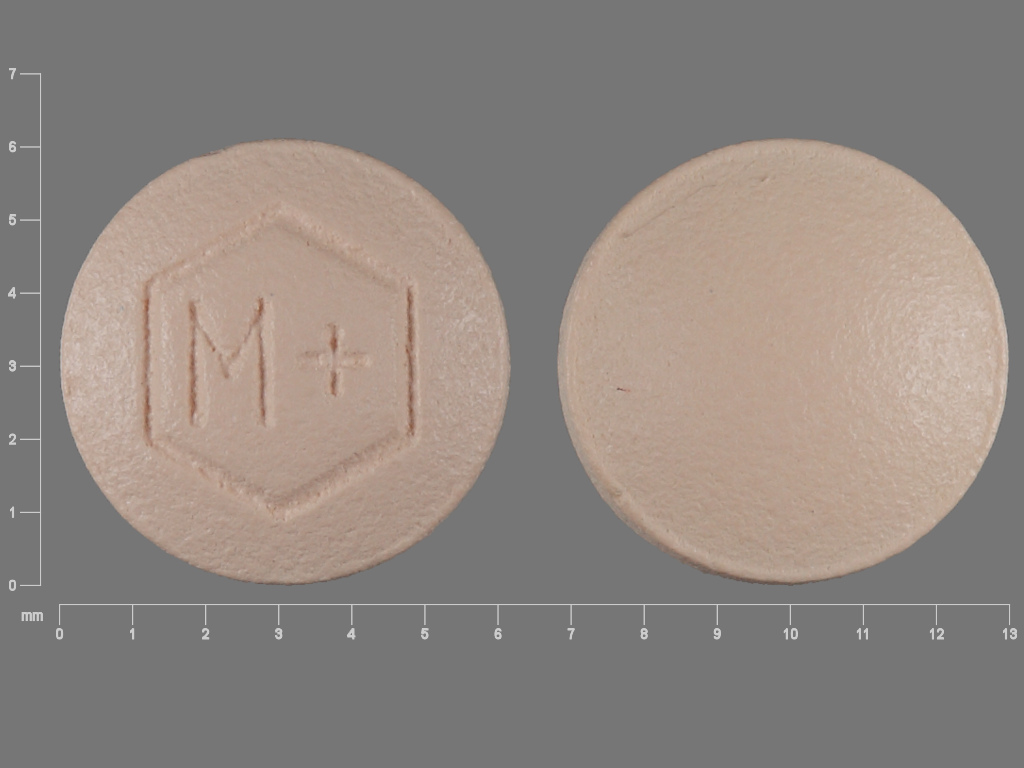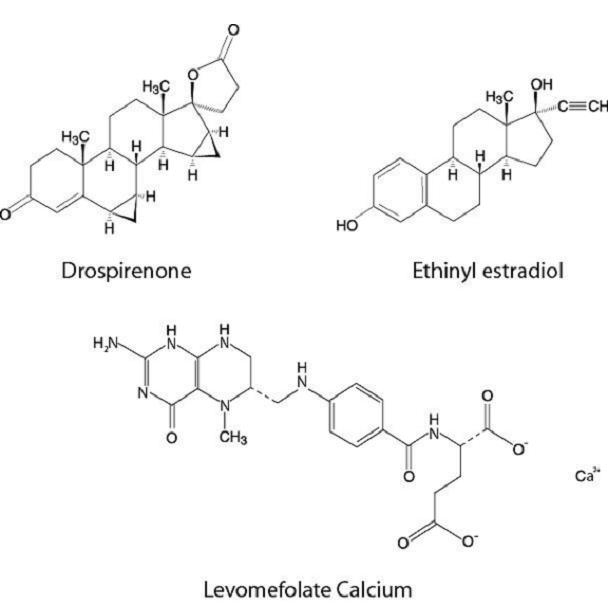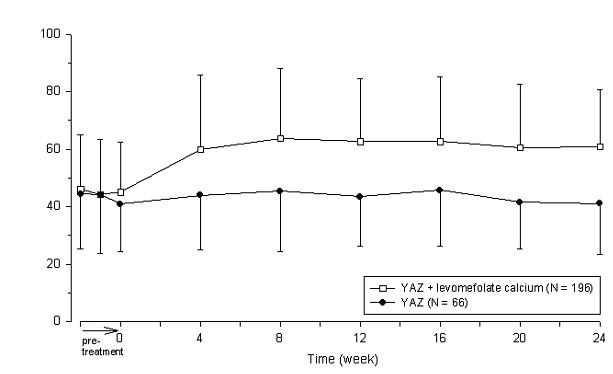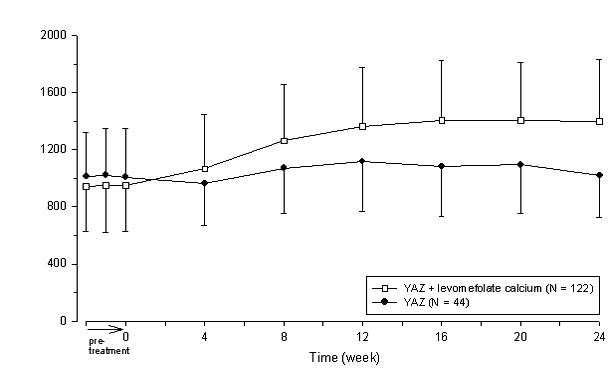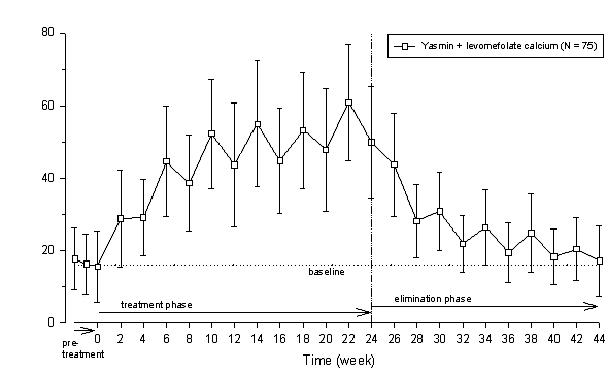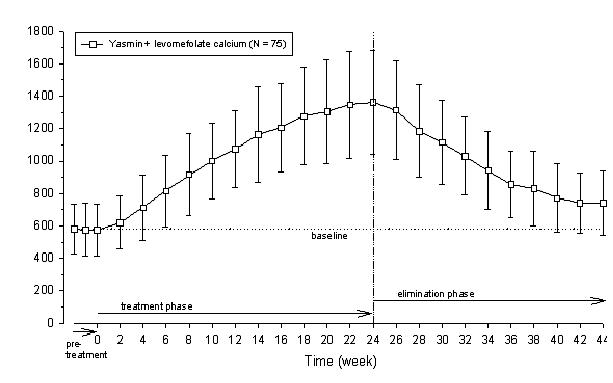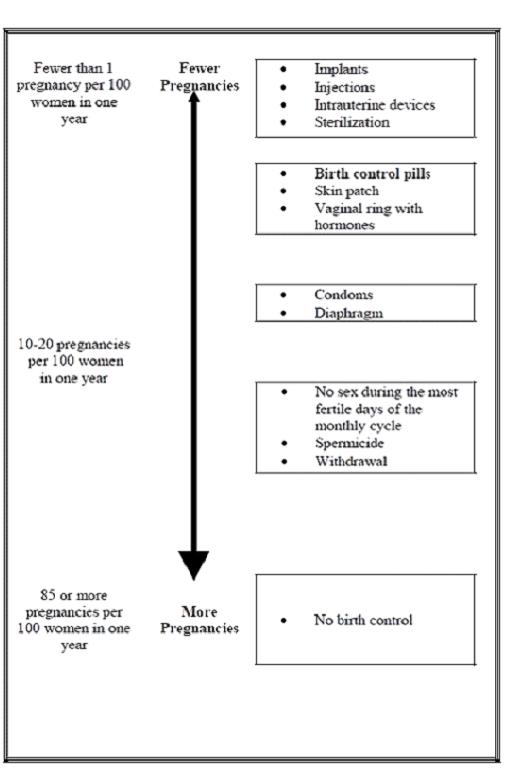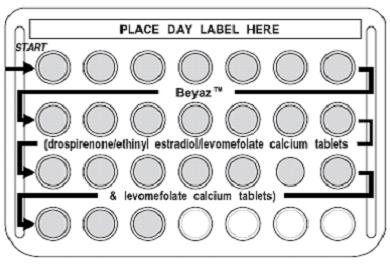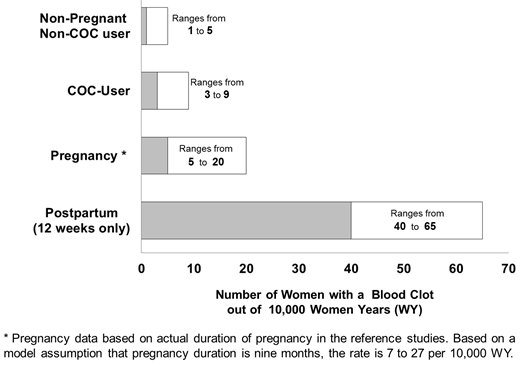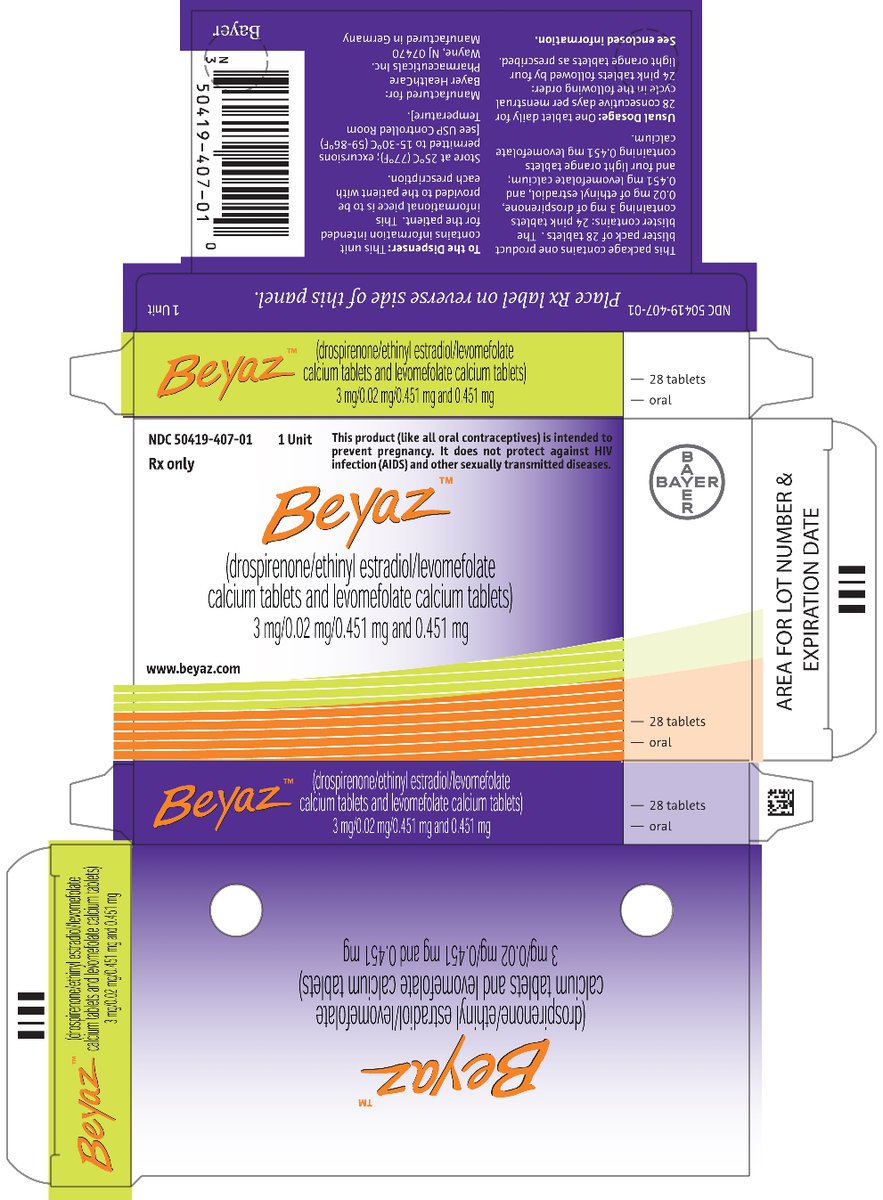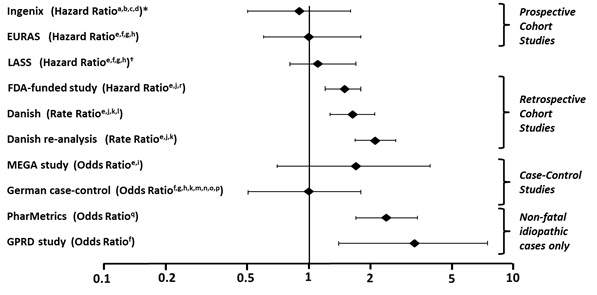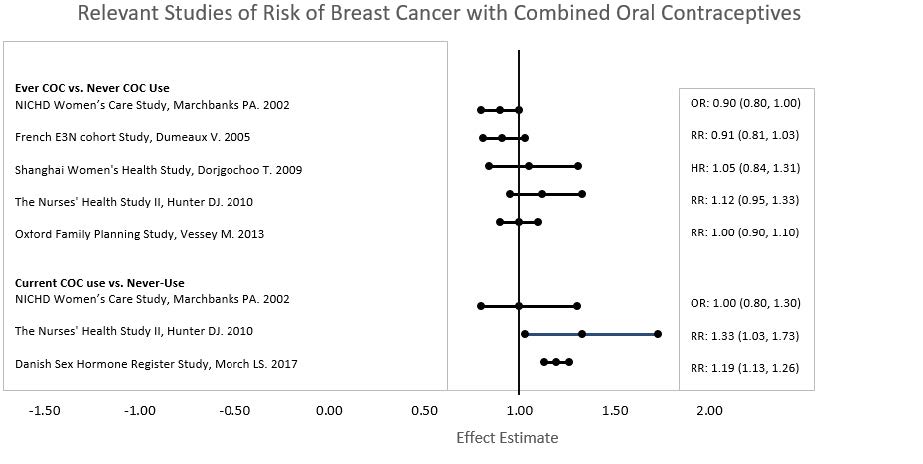 DRUG LABEL: Beyaz
NDC: 50419-407 | Form: KIT | Route: ORAL
Manufacturer: Bayer HealthCare Pharmaceuticals Inc.
Category: prescription | Type: HUMAN PRESCRIPTION DRUG LABEL
Date: 20230519

ACTIVE INGREDIENTS: DROSPIRENONE 3 mg/1 1; ETHINYL ESTRADIOL 0.02 mg/1 1; LEVOMEFOLATE CALCIUM 0.451 mg/1 1; LEVOMEFOLATE CALCIUM 0.451 mg/1 1
INACTIVE INGREDIENTS: FERRIC OXIDE RED; HYPROMELLOSE, UNSPECIFIED; LACTOSE MONOHYDRATE; MAGNESIUM STEARATE; TITANIUM DIOXIDE; BETADEX; MICROCRYSTALLINE CELLULOSE; CROSCARMELLOSE SODIUM; HYDROXYPROPYL CELLULOSE (1600000 WAMW); POLYETHYLENE GLYCOL, UNSPECIFIED; TALC; HYPROMELLOSE, UNSPECIFIED; LACTOSE MONOHYDRATE; MAGNESIUM STEARATE; TALC; TITANIUM DIOXIDE; MICROCRYSTALLINE CELLULOSE; CROSCARMELLOSE SODIUM; HYDROXYPROPYL CELLULOSE (1600000 WAMW); POLYETHYLENE GLYCOL, UNSPECIFIED; FERRIC OXIDE RED; FERRIC OXIDE YELLOW

HIGHLIGHTS OF PRESCRIBING INFORMATION

These highlights do not include all the information needed to use BEYAZ safely and effectively. See full prescribing information for BEYAZ.
BEYAZ (drospirenone/ethinyl estradiol/levomefolate calcium tablets and levomefolate calcium tablets), for oral use
Initial U.S. Approval: 2010

RECENT MAJOR CHANGES

Dosage and Administration (2.3) 5/2023

Contraindications, Pregnancy (4) Removed 5/2023

Warnings and Precautions (5.11) Removed 5/2023

WARNING: CIGARETTE SMOKING AND SERIOUS CARDIOVASCULAR EVENTS

See full prescribing information for complete boxed warning.

- Women over 35 years old who smoke should not use Beyaz. (4)
- Cigarette smoking increases the risk of serious cardiovascular events from combination oral contraceptive (COC) use. (4)

1 INDICATIONS AND USAGE

Beyaz is a combination of drospirenone, a progestin and ethinyl estradiol, an estrogen containing a folate, indicated for use by females of reproductive potential to:

- Prevent pregnancy. (1.1)
- Treat symptoms of premenstrual dysphoric disorder (PMDD) for females of reproductive potential who choose to use an oral contraceptive for contraception. (1.2)
- Treat moderate acne for females of reproductive potential at least 14 years old only if the patient desires an oral contraceptive for birth control. (1.3)
- Raise folate levels in females of reproductive potential who choose to use an oral contraceptive for contraception. (1.4)

2 DOSAGE AND ADMINISTRATION

- Take one tablet daily by mouth at the same time every day. (2.1)
- Tablets must be taken in the order directed on the blister pack. (2.1)

3 DOSAGE FORMS AND STRENGTHS

Beyaz consists of 28 film-coated, biconvex tablets in the following order (3):

- 24 pink tablets, each containing 3 mg drospirenone (DRSP), 0.02 mg ethinyl estradiol (EE) as betadex clathrate and 0.451 mg levomefolate calcium
- 4 light orange tablets, each containing 0.451 mg levomefolate calcium

4 CONTRAINDICATIONS

- Renal impairment (4)
- Adrenal insufficiency (4)
- A high risk of arterial or venous thrombotic diseases (4)
- Undiagnosed abnormal uterine bleeding (4)
- Breast cancer (4)
- Liver tumors or liver disease (4)
- Co-administration with Hepatitis C drug combinations containing ombitasvir, paritaprevir/ritonavir, with or without dasabuvir (4)

5 WARNINGS AND PRECAUTIONS

- Vascular risks: Stop Beyaz if a thrombotic event occurs. Stop at least 4 weeks before and through 2 weeks after major surgery. Start no earlier than 4 weeks after delivery, in women who are not breastfeeding. (5.1) COCs containing DRSP may be associated with a higher risk of venous thromboembolism (VTE) than COCs containing levonorgestrel or some other progestins. Before initiating Beyaz in a new COC user or a woman who is switching from a contraceptive that does not contain DRSP, consider the risks and benefits of a DRSP-containing COC in light of her risk of a VTE. (5.1)
- Hyperkalemia: DRSP has anti-mineralocorticoid activity. Do not use in patients predisposed to hyperkalemia. Check serum potassium concentration during the first treatment cycle in women on long-term treatment with medications that may increase serum potassium concentration. (5.2, 7.1, 7.2)
- Liver disease: Discontinue Beyaz if jaundice occurs. (5.4)
- High blood pressure: Do not prescribe Beyaz for women with uncontrolled hypertension or hypertension with vascular disease. (5.6)
- Carbohydrate and lipid metabolic effects: Monitor prediabetic and diabetic women taking Beyaz. Consider an alternate contraceptive method for women with uncontrolled dyslipidemia. (5.8)
- Headache: Evaluate significant change in headaches and discontinue Beyaz if indicated. (5.9)
- Uterine bleeding: Evaluate irregular bleeding or amenorrhea. (5.10)

6 ADVERSE REACTIONS

- The most frequent adverse reactions (≥ 2%) in contraception, acne and folate clinical trials are headache/migraine (5.9%), menstrual irregularities (4.1%), nausea/vomiting (3.5%) and breast pain/tenderness (3.2%). (6.1)
- The most frequent adverse reactions (≥ 2%) in PMDD clinical trials are menstrual irregularities (24.9%), nausea (15.8%), headache (13.0%), breast tenderness (10.5%), fatigue (4.2%), irritability (2.8%), decreased libido (2.8%), increased weight (2.5%), and affect lability (2.1%). (6.1)

To report SUSPECTED ADVERSE REACTIONS, contact Bayer HealthCare Pharmaceuticals Inc. at 1-888-842-2937 or FDA at 1-800-FDA-1088 or www.fda.gov/medwatch

7 DRUG INTERACTIONS

- Drugs or herbal products that induce certain enzymes (for example, CYP3A4) may decrease the effectiveness of COCs or increase breakthrough bleeding. Counsel patients to use a back-up or alternative method of contraception when enzyme inducers are used with COCs. (7.1)

8 USE IN SPECIFIC POPULATIONS

Lactation: Can reduce milk production in breast-feeding females (8.2)

FULL PRESCRIBING INFORMATION

WARNING: CIGARETTE SMOKING AND SERIOUS CARDIOVASCULAR EVENTS

Cigarette smoking increases the risk of serious cardiovascular events from combination oral contraceptives (COC) use. This risk increases with age, particularly in women over 35 years of age, and with the number of cigarettes smoked. For this reason, COCs should not be used by women who are over 35 years of age and smoke [see Contraindications (4)].

1 INDICATIONS AND USAGE

1.1 Oral Contraceptive

Beyaz® is indicated for use by females of reproductive potential to prevent pregnancy.

1.2 Premenstrual Dysphoric Disorder (PMDD)

Beyaz is also indicated for the treatment of symptoms of premenstrual dysphoric disorder (PMDD) in females of reproductive potential who choose to use an oral contraceptive as their method of contraception. The effectiveness of Beyaz for PMDD when used for more than three menstrual cycles has not been evaluated.

The essential features of PMDD according to the Diagnostic and Statistical Manual-4th edition (DSM-IV) include markedly depressed mood, anxiety or tension, affective lability, and persistent anger or irritability. Other features include decreased interest in usual activities, difficulty concentrating, lack of energy, change in appetite or sleep, and feeling out of control. Physical symptoms associated with PMDD include breast tenderness, headache, joint and muscle pain, bloating and weight gain. In this disorder, these symptoms occur regularly during the luteal phase and remit within a few days following onset of menses; the disturbance markedly interferes with work or school, or with usual social activities and relationships with others. Diagnosis is made by healthcare providers according to DSM-IV criteria, with symptomatology assessed prospectively over at least two menstrual cycles. In making the diagnosis, care should be taken to rule out other cyclical mood disorders.

Beyaz has not been evaluated for the treatment of premenstrual syndrome (PMS).

1.3 Acne

Beyaz is indicated for the treatment of moderate acne vulgaris in females of reproductive potential at least 14 years of age, who have no known contraindications to oral contraceptive therapy and have achieved menarche. Beyaz should be used for the treatment of acne only if the patient desires an oral contraceptive for birth control.

1.4 Folate Supplementation

Beyaz is indicated in females of reproductive potential who choose to use an oral contraceptive as their method of contraception, to raise folate levels for the purpose of reducing the risk of a neural tube defect in a pregnancy conceived while taking the product or shortly after discontinuing the product.

2 DOSAGE AND ADMINISTRATION

2.1 How to Take Beyaz

Take one tablet by mouth at the same time every day. The failure rate may increase when pills are missed or taken incorrectly.

To achieve maximum contraceptive and PMDD effectiveness, Beyaz must be taken as directed, in the order directed on the blister pack. Single missed pills should be taken as soon as remembered.

2.2 How to Start Beyaz

Instruct the patient to begin taking Beyaz either on the first day of her menstrual period (Day 1 Start) or on the first Sunday after the onset of her menstrual period (Sunday Start).

Day 1 Start

During the first cycle of Beyaz use, instruct the patient to take one pink Beyaz daily, beginning on Day 1 of her menstrual cycle. (The first day of menstruation is Day 1.) She should take one pink Beyaz daily for 24 consecutive days, followed by one light orange tablet daily on Days 25 through 28. Beyaz should be taken in the order directed on the package at the same time each day, preferably after the evening meal or at bedtime with some liquid, as needed. Beyaz can be taken without regard to meals. If Beyaz is first taken later than the first day of the menstrual cycle, Beyaz should not be considered effective as a contraceptive until after the first 7 consecutive days of product administration. Instruct the patient to use a non-hormonal contraceptive as back-up during the first 7 days. The possibility of ovulation and conception prior to initiation of medication should be considered.

Sunday Start

During the first cycle of Beyaz use, instruct the patient to take one pink Beyaz daily, beginning on the first Sunday after the onset of her menstrual period. She should take one pink Beyaz daily for 24 consecutive days, followed by one light orange tablet daily on Days 25 through 28. Beyaz should be taken in the order directed on the package at the same time each day, preferably after the evening meal or at bedtime with some liquid, as needed. Beyaz can be taken without regard to meals. Beyaz should not be considered effective as a contraceptive until after the first 7 consecutive days of product administration. Instruct the patient to use a non-hormonal contraceptive as back-up during the first 7 days. The possibility of ovulation and conception prior to initiation of medication should be considered.

The patient should begin her next and all subsequent 28-day regimens of Beyaz on the same day of the week that she began her first regimen, following the same schedule. She should begin taking her pink tablets on the next day after ingestion of the last light orange folate tablet, regardless of whether or not a menstrual period has occurred or is still in progress. Anytime a subsequent cycle of Beyaz is started later than the day following administration of the last light orange tablet, the patient should use another method of contraception until she has taken a pink Beyaz daily for seven consecutive days.

When switching from a different birth control pill

When switching from another birth control pill, Beyaz should be started on the same day that a new pack of the previous oral contraceptive would have been started.

When switching from a method other than a birth control pill

When switching from a transdermal patch or vaginal ring, Beyaz should be started when the next application would have been due. When switching from an injection, Beyaz should be started when the next dose would have been due. When switching from an intrauterine contraceptive or an implant, Beyaz should be started on the day of removal.

Withdrawal bleeding usually occurs within 3 days following the last pink tablet. If spotting or breakthrough bleeding occurs while taking Beyaz, instruct the patient to continue taking Beyaz by the regimen described above. Counsel her that this type of bleeding is usually transient and without significance; however, advise her that if the bleeding is persistent or prolonged, she should consult her healthcare provider.

Although the occurrence of pregnancy is low if Beyaz is taken according to directions, if withdrawal bleeding does not occur, consider the possibility of pregnancy. If the patient has not adhered to the prescribed dosing schedule (missed one or more active tablets or started taking them on a day later than she should have), consider the possibility of pregnancy at the time of the first missed period and take appropriate diagnostic measures. If the patient has adhered to the prescribed regimen and misses two consecutive periods, rule out pregnancy. Discontinue Beyaz if pregnancy is confirmed.

The risk of pregnancy increases with each active pink tablet missed. If breakthrough bleeding occurs following missed tablets, it will usually be transient and of no consequence. If the patient misses one or more light orange tablets, she should still be protected against pregnancy provided she begins taking a new cycle of pink tablets on the proper day.

For postpartum women who do not breastfeed or after a second trimester abortion, start Beyaz no earlier than 4 weeks postpartum due to the increased risk of thromboembolism. If the patient starts on Beyaz postpartum and has not yet had a period, evaluate for possible pregnancy, and instruct her to use an additional method of contraception until she has taken Beyaz for 7 consecutive days.

2.3 Missed Doses

Table 1: Instructions for Beyaz Missed Doses
If one pink active tablet is missed | Take it as soon as possible. Take the next tablet at the regular time. This means two tablets may be taken in one day. A back-up birth control method is not required if the patient has sex.
If two pink active tablets in a row are missed in Week 1 or Week 2 | Take two tablets as soon as possible and two tablets the next day. Then take one tablet a day until the pack is finished. Additional nonhormonal contraception (such as condoms and spermicide) should be used as back-up if the patient has sex within 7 days after missing tablets.
If two pink active tablets in a row are missed in Week 3 or Week 4 | Day 1 Start: Throw out the rest of the pack and start a new pack that same day.; Sunday Start: Keep taking one tablet every day until Sunday. On Sunday, throw out the rest of the pack and start a new pack that same day.; Additional nonhormonal contraception (such as condoms and spermicide) should be used as back-up if the patient has sex within 7 days after missing tablets. The patient may not have their period this month but this is expected. However, if they miss their period two months in a row, they should call their healthcare provider because they might be pregnant.
If three or more pink active tablets in a row are missed during any week | Day 1 Start: Throw out the rest of the pack and start a new pack that same day.; Sunday Start: Keep taking one tablet every day until Sunday. On Sunday, throw out the rest of the pack and start a new pack that same day.; Additional nonhormonal contraception (such as condoms and spermicide) should be used as back-up if the patient has sex within 7 days after missing tablets. The patient may not have their period this month but this is expected. However, if they miss their period two months in a row, they should call their healthcare provider because they might be pregnant.
If any of the four light orange inactive tablets are missed in Week 4: | Throw away the tablets that were missed.; Keep taking one tablet each day until the pack is empty. They do not need a back-up method.
Finally, if they are still not sure what to do about the tablets they have missed: | Use nonhormonal contraception (such as condoms and spermicides) anytime they have sex. Contact their healthcare provider and continue taking one active pink tablet each day until otherwise directed.

2.4 Advice in Case of Gastrointestinal Disturbances

In case of severe vomiting or diarrhea, absorption may not be complete and additional contraceptive measures should be taken. If vomiting occurs within 3-4 hours after tablet-taking, this can be regarded as a missed tablet.

2.5 Folate Supplementation

The U.S. Preventive Services Task Force recommends that women of childbearing age consume supplemental folic acid in a dose of at least 0.4 mg (400 mcg) daily.^1 Consider other folate supplementation that a woman may be taking before prescribing Beyaz. Ensure that folate supplementation is maintained if a woman discontinues Beyaz due to pregnancy.

3 DOSAGE FORMS AND STRENGTHS

Beyaz (drospirenone/ethinyl estradiol/levomefolate calcium tablets and levomefolate calcium tablets) is available in blister packs.

Each blister pack (28 film-coated tablets) contains in the following order:

- 24 pink tablets each containing 3 mg drospirenone (DRSP), 0.02 mg ethinyl estradiol (EE) as betadex clathrate and 0.451 mg levomefolate calcium
- 4 light orange tablets each containing 0.451 mg levomefolate calcium

4 CONTRAINDICATIONS

Beyaz is contraindicated in females who are known to have or develop the following conditions:

- Renal impairment
- Adrenal insufficiency
- A high risk of arterial or venous thrombotic diseases. Examples include women who are known to:
  - Smoke, if over age 35 [see Boxed Warning and Warnings and Precautions (5.1)]
  - Have deep vein thrombosis or pulmonary embolism, now or in the past [see Warnings and Precautions (5.1)]
  - Have cerebrovascular disease [see Warnings and Precautions (5.1)]
  - Have coronary artery disease [see Warnings and Precautions (5.1)]
  - Have thrombogenic valvular or thrombogenic rhythm diseases of the heart (for example, subacute bacterial endocarditis with valvular disease, or atrial fibrillation) [see Warnings and Precautions (5.1)]
  - Have inherited or acquired hypercoagulopathies [see Warnings and Precautions (5.1)]
  - Have uncontrolled hypertension [see Warnings and Precautions (5.6)]
  - Have diabetes mellitus with vascular disease [see Warnings and Precautions (5.8)]
  - Have headaches with focal neurological symptoms or have migraine headaches with or without aura if over age 35 [see Warnings and Precautions (5.9)]
- Undiagnosed abnormal uterine bleeding [see Warnings and Precautions (5.10)]
- Current diagnosis of, or history of, breast cancer, which may be hormone-sensitive [see Warnings and Precautions (5.3)]
- Liver tumors, benign or malignant, or liver disease [see Warnings and Precautions (5.4) and Use in Specific Populations (8.7
- Use of Hepatitis C drug combinations containing ombitasvir/paritaprevir/ritonavir, with or without dasabuvir due to the potential for ALT elevations [see Warnings and Precautions (5.5) and Drug Interactions (7.3)].

5 WARNINGS AND PRECAUTIONS

5.1 Thromboembolic Disorders and Other Vascular Problems

Stop Beyaz if an arterial or venous thrombotic (VTE) event occurs.

Based on presently available information on DRSP-containing COCs with 0.03 mg ethinyl estradiol (that is, Yasmin), DRSP-containing COCs may be associated with a higher risk of venous thromboembolism (VTE) than COCs containing the progestin levonorgestrel or some other progestins. Epidemiologic studies that compared the risk of VTE reported that the risk ranged from no increase to a three-fold increase. Before initiating use of Beyaz in a new COC user or a woman who is switching from a contraceptive that does not contain DRSP, consider the risks and benefits of a DRSP-containing COC in light of her risk of a VTE. Known risk factors for VTE include smoking, obesity, and family history of VTE, in addition to other factors that contraindicate use of COCs [see Contraindications (4)].

A number of studies have compared the risk of VTE for users of Yasmin (which contains 0.03 mg of EE and 3 mg of DRSP) to the risk for users of other COCs, including COCs containing levonorgestrel. Those that were required or sponsored by regulatory agencies are summarized in Table 2.

Table 2: Estimates (Hazard Ratios) of Venous Thromboembolism Risk in Current Users of Yasmin Compared to Users of Oral Contraceptives that Contain Other Progestins
Epidemiologic Study (Author, Year of Publication) Population Studied | Comparator Product (all are low-dose COCs; with ≤ 0.04 mg of EE) | Hazard Ratio (HR) (95% CI)
i3 Ingenix (Seeger 2007) Initiators, including new users ["New users" - no use of combination hormonal contraception for at least the prior 6 months] | All COCs available in the US during the conduct of the study [Includes low-dose COCs containing the following progestins: norgestimate, norethindrone, levonorgestrel, desogestrel, norgestrel, medroxyprogesterone, or ethynodiol diacetate] | HR: 0.9 (0.5-1.6)
EURAS (Dinger 2007) Initiators, including new users | All COCs available in Europe during the conduct of the study [Includes low-dose COCs containing the following progestins: levonorgestrel, desogestrel, dienogest, chlormadinone acetate, gestodene, cyproterone acetate, norgestimate, or norethindrone] | HR: 0.9 (0.6-1.4)
 | Levonorgestrel/EE | HR: 1.0 (0.6-1.8)
FDA-funded study” (2011)
New users | Other COCs available during the course of the study [Includes low-dose COCs containing the following progestins: norgestimate, norethindrone, or levonorgestrel] | HR: 1.8 (1.3-2.4)
 | Levonorgestrel/0.03 mg EE | HR: 1.6 (1.1-2.2)
All users (i.e., initiation and continuing use of study combination hormonal contraception) | Other COCs available during the course of the study | HR: 1.7 (1.4-2.1)
 | Levonorgestrel/0.03 mg EE | HR: 1.5 (1.2-1.8)

In addition to these “regulatory studies,” other studies of various designs have been conducted. Overall, there are two prospective cohort studies (see Table 2): the US post-approval safety study Ingenix [Seeger 2007], the European post-approval safety study EURAS (European Active Surveillance Study) [Dinger 2007]. An extension of the EURAS study, the Long-Term Active Surveillance Study (LASS), did not enroll additional subjects, but continued to assess VTE risk. There are three retrospective cohort studies: one study in the US funded by the FDA (see Table 2), and two from Denmark [Lidegaard 2009, Lidegaard 2011]. There are two case-control studies: the Dutch MEGA study analysis [van Hylckama Vlieg 2009] and the German case-control study [Dinger 2010]. There are two nested case-control studies that evaluated the risk of non-fatal idiopathic VTE: the PharMetrics study [Jick 2011] and the GPRD study [Parkin 2011]. The results of all of these studies are presented in Figure 1.

Figure 1: VTE Risk with Yasmin Relative to LNG-Containing COCs (adjusted risk#)

Risk ratios displayed on logarithmic scale; risk ratio < 1 indicates a lower risk of VTE for DRSP, > 1 indicates an increased risk of VTE for DRSP.

*Comparator “Other COCs”, including LNG- containing COCs

† LASS is an extension of the EURAS study

#Some adjustment factors are indicated by superscript letters: a) Current heavy smoking, b) hypertension, c) obesity, d) family history, e) age, f) BMI, g) duration of use, h) VTE history, i) period of inclusion, j) calendar year, k) education, l) length of use, m) parity, n) chronic disease, o) concomitant medication, p) smoking, q) duration of exposure, r) site

(References: Ingenix [Seeger 2007]^2, EURAS (European Active Surveillance Study) [Dinger 2007]^3, LASS (Long-Term Active Surveillance Study) [Dinger, unpublished document on file], FDA-funded study [Sidney 2011]^4, Danish [Lidegaard 2009]^5, Danish re-analysis [ Lidegaard 2011]^6, MEGA study [van Hylckama Vlieg 2009]^7, German Case-Control study [Dinger 2010]^8, PharMetrics [Jick 2011]^9, GPRD study [Parkin 2011]^10)

Although the absolute VTE rates are increased for users of hormonal contraceptives compared to non-users, the rates during pregnancy are even greater, especially during the post-partum period (see Figure 2). The risk of VTE in women using COCs has been estimated to be 3 to 9 per 10,000 woman-years. The risk of VTE is highest during the first year of use. Data from a large, prospective cohort safety study of various COCs suggest that this increased risk, as compared to that in non-COC users, is greatest during the first 6 months of COC use. Data from this safety study indicate that the greatest risk of VTE is present after initially starting a COC or restarting (following a 4 week or greater pill-free interval) the same or a different COC.

The risk of thromboembolic disease due to oral contraceptives gradually disappears after COC use is discontinued.

Figure 2 shows the risk of developing a VTE for women who are not pregnant and do not use oral contraceptives, for women who use oral contraceptives, for pregnant women, and for women in the postpartum period. To put the risk of developing a VTE into perspective: If 10,000 women who are not pregnant and do not use oral contraceptives are followed for one year, between 1 and 5 of these women will develop a VTE.

Figure 2: Likelihood of Developing a VTE

If feasible, stop Beyaz at least 4 weeks before and through 2 weeks after major surgery or other surgeries known to have an elevated risk of thromboembolism.

Start Beyaz no earlier than 4 weeks after delivery, in women who are not breastfeeding. The risk of postpartum thromboembolism decreases after the third postpartum week, whereas the risk of ovulation increases after the third postpartum week.

Use of COCs also increases the risk of arterial thromboses such as strokes and myocardial infarctions, especially in women with other risk factors for these events.

COCs have been shown to increase both the relative and attributable risks of cerebrovascular events (thrombotic and hemorrhagic strokes), although, in general, the risk is greatest among older (>35 years of age), hypertensive women who also smoke. COCs also increase the risk for stroke in women with other underlying risk factors.

Oral contraceptives must be used with caution in women with cardiovascular disease risk factors.

Stop Beyaz if there is unexplained loss of vision, proptosis, diplopia, papilledema, or retinal vascular lesions. Evaluate for retinal vein thrombosis immediately. [See Adverse Reactions (6).]

5.2 Hyperkalemia

Beyaz contains 3 mg of the progestin DRSP, which has anti-mineralocorticoid activity, including the potential for hyperkalemia in high-risk patients, comparable to a 25 mg dose of spironolactone. Beyaz is contraindicated in patients with conditions that predispose to hyperkalemia (that is, renal impairment, hepatic impairment, and adrenal insufficiency). Women receiving daily, long-term treatment for chronic conditions or diseases with medications that may increase serum potassium concentration should have their serum potassium concentration checked during the first treatment cycle. Medications that may increase serum potassium concentration include ACE inhibitors, angiotensin-II receptor antagonists, potassium-sparing diuretics, potassium supplementation, heparin, aldosterone antagonists, and NSAIDs. Consider monitoring serum potassium concentration in high-risk patients who take a strong CYP3A4 inhibitor long-term and concomitantly. Strong CYP3A4 inhibitors include azole antifungals (e.g. ketoconazole, itraconazole, voriconazole), HIV/HCV protease inhibitors (e.g., indinavir, boceprevir), and clarithromycin [see Clinical Pharmacology (12.3)].

5.3 Malignant Neoplasms

Breast Cancer

Beyaz is contraindicated in females who currently have or have had breast cancer because breast cancer may be hormonally sensitive [see Contraindications (4)].

Epidemiology studies have not found a consistent association between use of combined oral contraceptives (COCs) and breast cancer risk. Studies do not show an association between ever (current or past) use of COCs and risk of breast cancer. However, some studies report a small increase in the risk of breast cancer among current or recent users (<6 months since last use) and current users with longer duration of COC use [see Adverse Reactions (6.2)].

Cervical Cancer

Some studies suggest that COCs are associated with an increase in the risk of cervical cancer or intraepithelial neoplasia. However, there is controversy about the extent to which these findings may be due to differences in sexual behavior and other factors.

5.4 Liver Disease

Discontinue Beyaz if jaundice develops. Steroid hormones may be poorly metabolized in patients with impaired liver function. Acute or chronic disturbances of liver function may necessitate the discontinuation of COC use until markers of liver function return to normal and COC causation has been excluded.

Hepatic adenomas are associated with COC use. An estimate of the attributable risk is 3.3 cases/100,000 COC users. Rupture of hepatic adenomas may cause death through intra-abdominal hemorrhage.

Studies have shown an increased risk of developing hepatocellular carcinoma in long-term (> 8 years) COC users. However, the attributable risk of liver cancers in COC users is less than one case per million users.

Oral contraceptive-related cholestasis may occur in women with a history of pregnancy-related cholestasis. Women with a history of COC-related cholestasis may have the condition recur with subsequent COC use.

5.5 Risk of Liver Enzyme Elevations with Concomitant Hepatitis C Treatment

During clinical trials with the Hepatitis C combination drug regimen that contains ombitasvir/paritaprevir/ritonavir, with or without dasabuvir, ALT elevations greater than 5 times the upper limit of normal (ULN), including some cases greater than 20 times the ULN, were significantly more frequent in women using ethinyl estradiol-containing medications, such as COCs. Discontinue Beyaz prior to starting therapy with the combination drug regimen ombitasvir/paritaprevir/ritonavir, with or without dasabuvir [see Contraindications (4)]. Beyaz can be restarted approximately 2 weeks following completion of treatment with the Hepatitis C combination drug regimen.

5.6 High Blood Pressure

For women with well-controlled hypertension, monitor blood pressure and stop Beyaz if blood pressure rises significantly. Women with uncontrolled hypertension or hypertension with vascular disease should not use COCs.

An increase in blood pressure has been reported in women taking COCs, and this increase is more likely in older women and with extended duration of use. The incidence of hypertension increases with increasing concentration of progestin.

5.7 Gallbladder Disease

Studies suggest a small increased relative risk of developing gallbladder disease among COC users.

5.8 Carbohydrate and Lipid Metabolic Effects

Carefully monitor prediabetic and diabetic women who are taking Beyaz. COCs may decrease glucose tolerance in a dose-related fashion.

Consider alternative contraception for women with uncontrolled dyslipidemia. A small proportion of women will have adverse lipid changes while on COCs.

Women with hypertriglyceridemia, or a family history thereof, may be at an increased risk of pancreatitis when using COCs.

5.9 Headache

If a woman taking Beyaz develops new headaches that are recurrent, persistent, or severe, evaluate the cause and discontinue Beyaz if indicated.

An increase in frequency or severity of migraine during COC use (which may be prodromal of a cerebrovascular event) may be a reason for immediate discontinuation of the COC.

5.10 Bleeding Irregularities

Unscheduled (breakthrough or intracyclic) bleeding and spotting sometimes occur in patients on COCs, especially during the first three months of use. If bleeding persists or occurs after previously regular cycles, check for causes such as pregnancy or malignancy. If pathology and pregnancy are excluded, bleeding irregularities may resolve over time or with a change to a different COC.

Data for Beyaz show the average number of episodes of bleeding per reference period (90 days) was 3.2 in Cycles 4-6. The average number of bleeding and/or spotting days with Beyaz was 15.1 days. The intensity of bleeding for Beyaz based on the ratio of spotting-only days versus total bleeding and/or spotting days was 5.2/15.1 days.

Based on patient diaries from two contraceptive clinical trials of YAZ, 8 to 25% of women experienced unscheduled bleeding per 28-day cycle. A total of 12 subjects out of 1,056 (1.1%) discontinued YAZ due to menstrual disorders including intermenstrual bleeding, menorrhagia, and metrorrhagia.

Women who use Beyaz may experience absence of withdrawal bleeding, even if they are not pregnant. Based on subject diaries from YAZ contraception trials for up to 13 cycles, 6 to 10% of women experienced cycles with no withdrawal bleeding. Some women may encounter post-pill amenorrhea or oligomenorrhea, especially when such a condition was pre-existent.

If withdrawal bleeding does not occur, consider the possibility of pregnancy. If the patient has not adhered to the prescribed dosing schedule (missed one or more active tablets or started taking them on a day later than she should have), consider the possibility of pregnancy at the time of the first missed period and take appropriate diagnostic measures. If the patient has adhered to the prescribed regimen and misses two consecutive periods, rule out pregnancy.

5.11 Depression

Women with a history of depression should be carefully observed and Beyaz discontinued if depression recurs to a serious degree.

5.12 Interference with Laboratory Tests

The use of COCs may change the results of some laboratory tests, such as coagulation factors, lipids, glucose tolerance, and binding proteins. Women on thyroid hormone replacement therapy may need increased doses of thyroid hormone because serum concentrations of thyroid-binding globulin increase with use of COCs [see Drug Interactions (7.2)].

DRSP causes an increase in plasma renin activity and plasma aldosterone induced by its mild anti-mineralocorticoid activity.

Folates may mask vitamin B12 deficiency.

5.13 Monitoring

A woman who is taking COCs should have a yearly visit with her healthcare provider for a blood pressure check and for other indicated healthcare.

5.14 Other Conditions

In women with hereditary angioedema, exogenous estrogens may induce or exacerbate symptoms of angioedema. Chloasma may occasionally occur, especially in women with a history of chloasma gravidarum. Women with a tendency to chloasma should avoid exposure to the sun or ultraviolet radiation while taking COCs.

6 ADVERSE REACTIONS

The following serious adverse reactions with the use of COCs are discussed elsewhere in the labeling:

- Serious cardiovascular events and stroke [see Boxed Warning and Warnings and Precautions (5.1)]
- Vascular events [see Warnings and Precautions (5.1)]
- Liver disease [see Warnings and Precautions (5.4)]

6.1 Clinical Trials Experience

Because clinical trials are conducted under widely varying conditions, the adverse reaction rates observed cannot be directly compared to rates in other clinical trials and may not reflect the rates observed in practice.

Contraception, Acne and Folate Supplementation Clinical Trials

The data provided reflect the experience with the use of YAZ (3 mg DRSP/0.02 mg EE), in the adequate and well-controlled studies for contraception (N=1,056), for moderate acne vulgaris (N=536) and folate supplementation (N=379).

For contraception, a Phase 3, multicenter, multinational, open-label study was conducted to evaluate safety and efficacy up to one year in 1,027 women aged 17–36 who took at least one dose of YAZ. A second Phase 3 study was a single center, open-label, active-controlled study to evaluate the effect of 7 28-day cycles of YAZ on carbohydrate metabolism, lipids and hemostasis in 29 women aged 18–35. For acne, two multicenter, double-blind, randomized, placebo-controlled studies, in 536 women aged 14–45 with moderate acne vulgaris who took at least one dose of YAZ, evaluated the safety and efficacy during up to 6 cycles. For folate supplementation, the primary efficacy study using Beyaz was a multicenter, double-blind, randomized, active-controlled US trial in 379 healthy women aged 18–40 who were treated with Beyaz or YAZ for up to 24 weeks.

The adverse reactions seen across the 3 indications overlapped, and are reported using the frequencies from the pooled dataset. The most common adverse reactions (≥ 2% of users) were: headache/migraine (5.9%), menstrual irregularities (including vaginal hemorrhage [primarily spotting], metrorrhagia and menorrhagia) (4.1%), nausea/vomiting (3.5%), and breast pain/tenderness (3.2%).

PMDD Clinical Trials

Safety data from trials for the indication of PMDD are reported separately due to differences in study design and setting in the OC, Acne and Folate Supplementation studies as compared to the PMDD clinical program.

Two (one parallel and one crossover designed) multicenter, double-blind, randomized, placebo-controlled trials for the secondary indication of treating the symptoms of PMDD evaluated safety and efficacy of YAZ during up to 3 cycles among 285 women aged 18–42, diagnosed with PMDD and who took at least one dose of YAZ.

Common adverse reactions (≥ 2% of users) were: menstrual irregularities (including vaginal hemorrhage [primarily spotting] and metrorrhagia) (24.9%), nausea (15.8%), headache (13.0%), breast tenderness (10.5%), fatigue (4.2%), irritability (2.8%), decreased libido (2.8%), increased weight (2.5%), and affect lability (2.1%).

Adverse Reactions (≥1%) Leading to Study Discontinuation:

Contraception Clinical Trials

Of 1,056 women, 6.6% discontinued from the clinical trials due to an adverse reaction; the most frequent adverse reactions leading to discontinuation were headache/migraine (1.6%) and nausea/vomiting (1.0%).

Acne Clinical Trials

Of 536 women, 5.4% discontinued from the clinical trials due to an adverse reaction; the most frequent adverse reaction leading to discontinuation was menstrual irregularities (including menometrorrhagia, menorrhagia, metrorrhagia and vaginal hemorrhage) (2.2%) .

Folate Clinical Trial

Of 285 women, 4.6% who used Beyaz or YAZ discontinued from the clinical trials due to an adverse reaction; no reaction leading to discontinuation occurred in ≥ 1% of women.

PMDD Clinical Trials

Of 285 women, 11.6% discontinued from the clinical trials due to an adverse reaction; the most frequent adverse reactions leading to discontinuation were: nausea/vomiting (4.6%), menstrual irregularity (including vaginal hemorrhage, menorrhagia, menstrual disorder, menstruation irregular and metrorrhagia) (4.2%), fatigue (1.8%), breast tenderness (1.4%), depression (1.4%), headache (1.1%), and irritability (1.1%).

Serious Adverse Reactions

Contraception Clinical Trials: migraine and cervical dysplasia

Acne Clinical Trials: none reported in the clinical trials

Folate Supplementation Clinical Trial: cervix carcinoma stage 0

PMDD Clinical Trials: cervical dysplasia

6.2 Postmarketing Experience

Five studies that compared breast cancer risk between ever-users (current or past use) of COCs and never-users of COCs reported no association between ever use of COCs and breast cancer risk, with effect estimates ranging from 0.90 - 1.12 (Figure 3).

Three studies compared breast cancer risk between current or recent COC users (<6 months since last use) and never users of COCs (Figure 3). One of these studies reported no association between breast cancer risk and COC use. The other two studies found an increased relative risk of 1.19 - 1.33 with current or recent use. Both of these studies found an increased risk of breast cancer with current use of longer duration, with relative risks ranging from 1.03 with less than one year of COC use to approximately 1.4 with more than 8-10 years of COC use.

Figure 3: Relative Studies of Risk of Breast Cancer with Combined Oral Contraceptives

RR = relative risk; OR = odds ratio; HR = hazard ratio. “ever COC” are females with current or past COC use; “never COC use” are females that never used COCs.

The following adverse reactions have been identified during post approval use of YAZ. Because these reactions are reported voluntarily from a population of uncertain size, it is not always possible to reliably estimate their frequency or establish a causal relationship to drug exposure.

Adverse reactions are grouped into System Organ Classes, and ordered by frequency.

Vascular disorders: Venous and arterial thromboembolic events (including pulmonary emboli, deep vein thrombosis, cerebral thrombosis, retinal thrombosis, myocardial infarction and stroke), hypertension (including hypertensive crisis)

Hepatobiliary disorders: Gallbladder disease, liver function disturbances, liver tumors

Immune system disorders: Hypersensitivity (including anaphylactic reaction)

Metabolism and nutrition disorders: Hyperkalemia, hypertriglyceridemia, changes in glucose tolerance or effect on peripheral insulin resistance (including diabetes mellitus)

Skin and subcutaneous tissue disorders: Chloasma, angioedema, erythema nodosum, erythema multiforme

Gastrointestinal disorders: Inflammatory bowel disease

Musculoskeletal and connective tissue disorders: Systemic lupus erythematosus

7 DRUG INTERACTIONS

Consult the labeling of all concurrently-used drugs to obtain further information about interactions with hormonal contraceptives or the potential for enzyme alterations.

7.1 Effects of Other Drugs on Combined Oral Contraceptives

Substances diminishing the efficacy of COCs: Drugs or herbal products that induce certain enzymes, including cytochrome P450 3A4 (CYP3A4), may decrease the effectiveness of COCs or increase breakthrough bleeding. Some drugs or herbal products that may decrease the effectiveness of hormonal contraceptives include phenytoin, barbiturates, carbamazepine, bosentan, felbamate, griseofulvin, oxcarbazepine, rifampin, topiramate and products containing St. John’s wort. Interactions between oral contraceptives and other drugs may lead to breakthrough bleeding and/or contraceptive failure. Counsel women to use an alternative method of contraception or a back-up method when enzyme inducers are used with COCs, and to continue back-up contraception for 28 days after discontinuing the enzyme inducer to ensure contraceptive reliability.

Substances increasing the plasma concentrations of COCs: Co-administration of atorvastatin and certain COCs containing EE increase AUC values for EE by approximately 20%. Ascorbic acid and acetaminophen may increase plasma EE concentrations, possibly by inhibition of conjugation.

Concomitant administration of moderate or strong CYP3A4 inhibitors such as azole antifungals (e.g., ketoconazole, itraconazole, voriconazole, fluconazole), verapamil, macrolides (e.g., clarithromycin, erythromycin), diltiazem, and grapefruit juice can increase the plasma concentrations of the estrogen or the progestin or both. In a clinical drug-drug interaction study conducted in premenopausal women, once daily co-administration of DRSP 3 mg/EE 0.02 mg containing tablets with strong CYP3A4 inhibitor, ketoconazole 200 mg twice daily for 10 days resulted in a moderate increase of DRSP systemic exposure. The exposure of EE was increased mildly [see Warnings and Precautions (5.2) and Clinical Pharmacology (12.3)].

Human immunodeficiency virus (HIV)/Hepatitis C virus (HCV) protease inhibitors and non-nucleoside reverse transcriptase inhibitors: Significant changes (increase or decrease) in the plasma concentrations of estrogen and progestin have been noted in some cases of co-administration with HIV/HCV protease inhibitors or with non-nucleoside reverse transcriptase inhibitors.

Antibiotics: There have been reports of pregnancy while taking hormonal contraceptives and antibiotics, but clinical pharmacokinetic studies have not shown consistent effects of antibiotics on plasma concentrations of synthetic steroids.

7.2 Effects of Combined Oral Contraceptives on Other Drugs

COCs containing EE may inhibit the metabolism of other compounds. COCs have been shown to significantly decrease plasma concentrations of lamotrigine, likely due to induction of lamotrigine glucuronidation. This may reduce seizure control; therefore, dosage adjustments of lamotrigine may be necessary. Consult the labeling of the concurrently-used drug to obtain further information about interactions with COCs or the potential for enzyme alterations.

COCs Increasing the Plasma Concentrations of CYP450 Enzymes: In clinical studies, administration of a hormonal contraceptive containing EE did not lead to any increase or only to a weak increase in plasma concentrations of CYP3A4 substrates (e.g., midazolam) while plasma concentrations of CYP2C19 substrates (e.g., omeprazole and voriconazole) and CYP1A2 substrates (e.g., theophylline and tizanidine) can have a weak or moderate increase.

Clinical studies did not indicate an inhibitory potential of DRSP towards human CYP enzymes at clinically relevant concentrations [see Clinical Pharmacology (12.3)].

Women on thyroid hormone replacement therapy may need increased doses of thyroid hormone because serum concentration of thyroid-binding globulin increases with use of COCs.

Potential to Increase Serum Potassium Concentration: There is a potential for an increase in serum potassium concentration in women taking Beyaz with other drugs that may increase serum potassium concentration [see Warnings and Precautions (5.2) and Clinical Pharmacology (12.3)].

7.3 Concomitant Use with HCV Combination Therapy – Liver Enzyme Elevation

Do not co-administer Beyaz with HCV drug combinations containing ombitasvir/paritaprevir/ritonavir, with or without dasabuvir, due to potential for ALT elevations [see Warnings and Precautions (5.5)].

7.4 Effects of Folates on Other Drugs

Folates may modify the pharmacokinetics or pharmacodynamics of certain antifolate drugs, e.g., antiepileptics (such as phenytoin), methotrexate or pyrimethamine, and may result in a decreased pharmacological effect of the antifolate drug.

7.5 Effects of Other Drugs on Folates

Several drugs have been reported to reduce folate concentrations by inhibition of the dihydrofolate reductase enzyme (e.g., methotrexate and sulfasalazine) or by reducing folate absorption (e.g., cholestyramine), or via unknown mechanisms (e.g., antiepileptics such as carbamazepine, phenytoin, phenobarbital, primidone and valproic acid).

7.6 Interference with Laboratory Tests

The use of contraceptive steroids may influence the results of certain laboratory tests, such as coagulation factors, lipids, glucose tolerance, and binding proteins. DRSP causes an increase in plasma renin activity and plasma aldosterone induced by its mild anti-mineralocorticoid activity. Folates may mask vitamin B12 deficiency. [See Warnings and Precautions (5.12) and Drug Interactions (7.2).]

8 USE IN SPECIFIC POPULATIONS

8.1 Pregnancy

Risk Summary

There is no use for contraception in pregnancy; therefore, Beyaz should be discontinued during pregnancy. Epidemiologic studies and meta-analyses have not found an increased risk of genital or non-genital birth defects (including cardiac anomalies and limb-reduction defects) following exposure to CHCs before conception or during early pregnancy. In the U.S. general population, the estimated background risk of major birth defects and miscarriage in clinically recognized pregnancies is 2 to 4 percent and 15 to 20 percent, respectively.

Data

Human Data

A retrospective database study of women in Norway, that included 44,734 pregnancies of which 368 were women who inadvertently took drospirenone/ethinyl estradiol during the first trimester of a pregnancy, found there were no adverse effects on pre-term birth, small for gestational age, or birth weight Z-scores.

Post-marketing adverse event data on the use of Beyaz in pregnant women suggest that frequencies of miscarriage and congenital anomalies were not higher than the estimated background risk in the general population.

8.2 Lactation

Risk Summary

DRSP is present in human milk. After a single oral administration of 3 mg DRSP/0.03 mg EE tablets, DRSP concentration in breast milk over the 24-h period ranged from 1.4 to 7.0 ng/mL, with a mean ± standard deviation value of 3.7 ± 1.9 ng/mL.The estimated mean infant dose was 0.003 mg/day, which is about 0.1% of maternal dose (see Data). There is limited information on the effects of Beyaz on the breast-fed infant. CHCs can reduce milk production in breast-feeding females. This reduction can occur at any time but is less likely to occur once breast-feeding is well-established. When possible, advise the nursing female to use other methods of contraception until she discontinues breast-feeding. [See also Dosage and Administration (2.2)]. Increase in folate concentration in milk is not expected (see Data).

The developmental and health benefits of breast-feeding should be considered along with the mother’s clinical need for Beyaz and any potential adverse effects on the breast-fed child from Beyaz or from the underlying maternal condition.

Data

Human Data

An open-label study evaluated the degree of DRSP transfer into milk within 72 hours following a single oral administration of 3 mg DRSP/0.03 mg EE tablets to 6 healthy lactating women who were 1 week to 3 months post-partum. DRSP was present in breast milk with a mean Cmax of 13.5 ng/mL, while the mean Cmax in serum of lactating women was 30.8 ng/mL. The DRSP concentration in breast milk over the 24-hour period following dosing ranged from 1.4 to 7.0 ng/mL, with a mean ± standard deviation value of 3.7 ± 1.9 ng/mL. Based on single dose data, the maximal daily infant dose of DRSP was calculated to be 0.003 mg/day, which represented a mean of 0.1% of the maternal dose.

A study in approximately 60 lactating women demonstrated no significant differences in folate concentrations in milk between women who received 416mcg/day [6S]-5-methyltetrahydrofolate or 400 mcg/day folic acid and women who received placebo over a 16 week period. Studies to date indicate there is no adverse effect of folate on nursing infants.

8.4 Pediatric Use

Safety and efficacy of Beyaz has been established in women of reproductive age. Efficacy is expected to be the same for postpubertal adolescents under the age of 18 and for users 18 years and older. Use of this product before menarche is not indicated.

8.5 Geriatric Use

Beyaz has not been studied in postmenopausal women and is not indicated in this population.

8.6 Patients with Renal Impairment

Beyaz is contraindicated in patients with renal impairment [see Contraindications (4) and Warnings and Precautions (5.2)].

In subjects with creatinine clearance (CLcr) of 50–79 mL/min, serum DRSP concentrations were comparable to those in a control group with CLcr ≥ 80 mL/min. In subjects with CLcr of 30–49 mL/min, serum DRSP concentrations were on average 37% higher than those in the control group. In addition, there is a potential to develop hyperkalemia in subjects with renal impairment whose serum potassium is in the upper reference range, and who are concomitantly using potassium-sparing drugs [see Clinical Pharmacology (12.3)].

8.7 Patients with Hepatic Impairment

Beyaz is contraindicated in patients with hepatic disease [see Contraindications (4) and Warnings and Precautions (5.4)]. The mean exposure to DRSP in women with moderate liver impairment is approximately three times higher than the exposure in women with normal liver function. Beyaz has not been studied in women with severe hepatic impairment.

8.8 Race

No clinically significant difference was observed between the pharmacokinetics of DRSP or EE in Japanese versus Caucasian women [see Clinical Pharmacology (12.3)].

10 OVERDOSAGE

There have been no reports of serious ill effects from overdose, including ingestion by children. Overdosage may cause withdrawal bleeding in females and nausea.

DRSP is a spironolactone analogue which has anti-mineralocorticoid properties. Serum concentration of potassium and sodium, and evidence of metabolic acidosis, should be monitored in cases of overdose.

Levomefolate calcium doses of 17 mg/day (37-fold higher than the levomefolate calcium dose of Beyaz) were well tolerated after long-term treatment up to 12 weeks.

11 DESCRIPTION

Beyaz (drospirenone/ethinyl estradiol/levomefolate calcium tablets and levomefolate calcium tablets) provides an oral contraceptive regimen consisting of 28 film-coated tablets that contain the active ingredients specified for each tablet below:

- 24 pink tablets each containing 3 mg DRSP, 0.02 mg EE as betadex clathrate, and 0.451 mg levomefolate calcium
- 4 light orange tablets each containing 0.451 mg levomefolate calcium

The inactive ingredients in the pink tablets are lactose monohydrate NF, microcrystalline cellulose NF, croscarmellose sodium NF, hydroxypropyl cellulose NF, magnesium stearate NF, hypromellose USP, titanium dioxide USP, talc USP, polyethylene glycol NF, ferric oxide pigment, red NF. The light orange film-coated tablets contain 0.451 mg of levomefolate calcium. The inactive ingredients in the light orange tablets are lactose monohydrate NF, microcrystalline cellulose NF, croscarmellose sodium NF, hydroxypropyl cellulose NF, magnesium stearate NF, hypromellose USP, titanium dioxide USP talc USP, polyethylene glycol NF, ferric oxide pigment, red NF, ferric oxide pigment, yellow NF.

Drospirenone (6R,7R,8R,9S,10R,13S,14S,15S,16S,17S)-1,3',4',6,6a,7,8,9,10,11,12,13,14,15,15a,16-hexadecahydro-10,13-dimethylspiro-[17H-dicyclopropa- [6,7:15,16] cyclopenta[a]phenanthrene-17,2'(5H)-furan]-3,5'(2H)-dione) is a synthetic progestational compound and has a molecular weight of 366.5 and a molecular formula of C24H30O3.

Ethinyl estradiol (19-nor-17α-pregna 1,3,5(10)-triene-20-yne-3, 17-diol) is a synthetic estrogenic compound and has a molecular weight of 296.4 and a molecular formula of C20H24O2.

Levomefolate calcium (N-[4-[[(2-amino-1,4,5,6,7,8-hexahydro-5-methyl-4-oxo-(6S)-pteridinyl)methyl]amino]benzoyl]-L-glutamic acid, calcium salt) is a synthetic calcium salt of L-5-methyltetrahydrofolate (L-5-methyl-THF), which is a metabolite of vitamin B9 and has a molecular weight of 497.5 and a molecular formula of C20H23CaN7O6.

The structural formulas are as follows:

12 CLINICAL PHARMACOLOGY

12.1 Mechanism of Action

COCs lower the risk of becoming pregnant primarily by suppressing ovulation.

12.2 Pharmacodynamics

Drospirenone is a spironolactone analogue with anti-mineralocorticoid and antiandrogenic activity. The estrogen in Beyaz is ethinyl estradiol (EE).

Contraception

No specific pharmacodynamic studies were conducted with Beyaz.

Two studies evaluated the effect of 3 mg DRSP / 0.02 mg EE combinations on the suppression of ovarian activity as assessed by measurement of follicle size via transvaginal ultrasound and serum hormone (progesterone and estradiol) analyses during two treatment cycles (21-day active tablet period plus 7-day pill-free period). More than 90% of subjects in these studies demonstrated ovulation inhibition. One study compared the effect of 3 mg DRSP/0.02 mg EE combinations with two different regimens (24-day active tablet period plus 4-day pill-free period vs. 21-day active tablet period plus 7-day pill-free period) on the suppression of ovarian activity during two treatment cycles. During the first treatment cycle, there were no subjects (0/49, 0%) taking the 24-day regimen who ovulated compared to 1 subject (1/50, 2%) using the 21-day regimen. After intentionally introduced dosing errors (3 missed active tablets on Days 1 to 3) during the second treatment cycle, there was 1 subject (1/49, 2%) taking the 24-day regimen who ovulated compared to 4 subjects (4/50, 8%) using the 21-day regimen.

Acne

Acne vulgaris is a skin condition with a multifactorial etiology including androgen stimulation of sebum production. While the combination of EE and DRSP increases sex hormone binding globulin (SHBG) and decreases free testosterone, the relationship between these changes and a decrease in the severity of facial acne in otherwise healthy women with this skin condition has not been established. The impact of the antiandrogenic activity of DRSP on acne is not known.

Folate Supplementation

Two studies evaluated the impact of Beyaz on plasma folate and RBC folate levels. A randomized, double-blind, active-controlled, parallel group study compared plasma folate and red blood cell (RBC) folate levels during a 24-week treatment with YAZ + 0.451 mg levomefolate calcium as compared to YAZ alone in a U.S. population. The pharmacodynamic effect on plasma folate, RBC folate, and the profile of circulating folate metabolites was assessed during 24 weeks of treatment with 0.451 mg levomefolate calcium or with 0.4 mg folic acid (equimolar dose to 0.451 mg levomefolate calcium), both in combination with 3 mg DRSP/0.03 mg EE (Yasmin) followed by 20 weeks of open-label treatment with Yasmin only (elimination phase). [See Clinical Studies (14.4).]

12.3 Pharmacokinetics

Absorption

Beyaz and YAZ are bioequivalent with respect to DRSP and EE.

The absolute bioavailability of DRSP from a single entity tablet is about 76%. The absolute bioavailability of EE is approximately 40% as a result of presystemic conjugation and first-pass metabolism. The absolute bioavailability of Beyaz, which is a combination tablet of DRSP and EE stabilized by betadex as a clathrate (molecular inclusion complex), has not been evaluated. The bioavailability of EE is similar when dosed via a betadex clathrate formulation compared to when it is dosed as a free steroid. Serum concentrations of DRSP and EE reached peak levels within 1-2 hours after administration of Beyaz.

The pharmacokinetics of DRSP are dose proportional following single doses ranging from 1-10 mg. Following daily dosing of YAZ, steady state DRSP concentrations were observed after 8 days. There was about 2 to 3 fold accumulation in serum Cmax and AUC (0-24h) values of DRSP following multiple dose administration of YAZ (see Table 3).

For EE, steady-state conditions are reported during the second half of a treatment cycle. Following daily administration of YAZ, serum Cmax and AUC (0-24h) values of EE accumulate by a factor of about 1.5 to 2 (see Table 3).

Levomefolate calcium is structurally identical to L-5-methyltetrahydrofolate (L-5-methyl-THF), a metabolite of vitamin B9. Mean baseline concentrations of about 15 nmol/L are reached in populations without folate food fortification under normal nutritional conditions. Orally administered levomefolate calcium is absorbed and incorporated into the body folate pool. Peak plasma concentrations of about 50 nmol/L above baseline are reached within 0.5 – 1.5 hours after single oral administration of 0.451 mg levomefolate calcium.

Steady state conditions for total folate in plasma after intake of 0.451 mg levomefolate calcium are reached after about 8-16 weeks depending on the baseline levels. In red blood cells achievement of steady state is delayed due to the long life-span of red blood cells of about 120 days.

Table 3: Pharmacokinetic Parameters of YAZ (DRSP 3 mg and EE 0.02 mg)
DRSP
Cycle / Day | No. of Subjects | Cmax [geometric mean (geometric coefficient of variation)] (ng/mL) | Tmax [median (range)] (h) | AUC(0-24h) (ng•h/mL) | t1/2 (h)
1/1 | 23 | 38.4 (25) | 1.5 (1-2) | 268 (19) | NA [NA = Not available]
1/21 | 23 | 70.3 (15) | 1.5 (1-2) | 763 (17) | 30.8 (22)
EE
Cycle / Day | No. of Subjects | Cmax (pg/mL) | Tmax (h) | AUC(0-24h) (pg•h/mL) | t1/2 (h)
1/1 | 23 | 32.8 (45) | 1.5 (1-2) | 108 (52) | NA
1/21 | 23 | 45.1 (35) | 1.5 (1-2) | 220 (57) | NA

Food Effect

The rate of absorption of DRSP and EE following single administration of a formulation similar to Beyaz was slower under fed (high fat meal) conditions with the serum Cmax being reduced about 40% for both components. The extent of absorption of DRSP, however, remained unchanged. In contrast, the extent of absorption of EE was reduced by about 20% under fed conditions.

The effect of food on absorption of levomefolate calcium following administration of Beyaz has not been evaluated.

Distribution

DRSP and EE serum concentrations decline in two phases. The apparent volume of distribution of DRSP is approximately 4 L/kg and that of EE is reported to be approximately 4–5 L/kg.

DRSP does not bind to sex hormone binding globulin (SHBG) or corticosteroid binding globulin (CBG) but binds about 97% to other serum proteins. Multiple dosing over 3 cycles resulted in no change in the free fraction (as measured at trough concentrations). EE is reported to be highly but non-specifically bound to serum albumin (approximately 98.5 %) and induces an increase in the serum concentrations of both SHBG and CBG. EE induced effects on SHBG and CBG were not affected by variation of the DRSP dosage in the range of 2 to 3 mg.

Biphasic kinetics is reported for folates with a fast- and a slow-turnover pool. The fast turnover pool, probably reflecting newly absorbed folate, is consistent with the terminal half-life of approximately 4 – 5 hours after single oral administration of 0.451 mg levomefolate calcium. The slow-turnover pool reflecting turnover of folate polyglutamate has a mean residence time of greater than or equal to 100 days.

Metabolism

The two main metabolites of DRSP found in human plasma were identified to be the acid form of DRSP generated by opening of the lactone ring and the 4,5-dihydrodrospirenone-3-sulfate, formed by reduction and subsequent sulfatation. These metabolites were shown not to be pharmacologically active. Drospirenone is also subject to oxidative metabolism catalyzed by CYP3A4.

EE has been reported to be subject to significant gut and hepatic first-pass metabolism. Metabolism of EE and its oxidative metabolites occur primarily by conjugation with glucuronide or sulfate. CYP3A4 in the liver is responsible for the 2-hydroxylation which is the major oxidative reaction. The 2-hydroxy metabolite is further transformed by methylation and glucuronidation prior to urinary and fecal excretion.

L-5-methyl-THF is the predominant folate transport form in blood under physiological conditions and during folic acid and levomefolate calcium administration.

Excretion

DRSP serum concentrations are characterized by a terminal disposition phase half-life of approximately 30 hours after both single and multiple dose regimens. Excretion of DRSP was nearly complete after ten days and amounts excreted were slightly higher in feces compared to urine. DRSP was extensively metabolized and only trace amounts of unchanged DRSP were excreted in urine and feces. At least 20 different metabolites were observed in urine and feces. About 38-47% of the metabolites in urine were glucuronide and sulfate conjugates. In feces, about 17-20% of the metabolites were excreted as glucuronides and sulfates.

For EE the terminal disposition phase half-life has been reported to be approximately 24 hours. EE is not excreted unchanged. EE is excreted in the urine and feces as glucuronide and sulfate conjugates and undergoes enterohepatic circulation.

L-5-methyl-THF is eliminated from the body by urinary excretion of intact folates and catabolic products as well as fecal excretion through a biphasic kinetics process.

Use in Specific Populations

Pediatric Use: Safety and efficacy of Beyaz has been established in women of reproductive age. Efficacy is expected to be the same for postpubertal adolescents under the age of 18 and for users 18 years and older. Use of this product before menarche is not indicated.

Geriatric Use: Beyaz has not been studied in postmenopausal women and is not indicated in this population.

Race: No clinically significant difference was observed between the pharmacokinetics of DRSP or EE in Japanese versus Caucasian women (age 25-35) when 3 mg DRSP/0.02 mg EE was administered daily for 21 days. Other ethnic groups have not been specifically studied.

Renal Impairment: Beyaz is contraindicated in patients with renal impairment.

The effect of renal impairment on the pharmacokinetics of DRSP (3 mg daily for 14 days) and the effect of DRSP on serum potassium concentrations were investigated in three separate groups of female subjects (n=28, age 30-65). All subjects were on a low potassium diet. During the study, 7 subjects continued the use of potassium-sparing drugs for the treatment of their underlying illness. On the 14th day (steady-state) of DRSP treatment, the serum DRSP concentrations in the group with CLcr of 50–79 mL/min were comparable to those in the control group with CLcr ≥ 80 mL/min. The serum DRSP concentrations were on average 37% higher in the group with CLcr of 30–49 mL/min compared to those in the control group. DRSP treatment did not show any clinically significant effect on serum potassium concentration. Although hyperkalemia was not observed in the study, in five of the seven subjects who continued use of potassium-sparing drugs during the study, mean serum potassium concentrations increased by up to 0.33 mEq/L. [See Contraindications (4), and Warnings and Precautions (5.2).]

Hepatic Impairment: Beyaz is contraindicated in patients with hepatic disease.

The mean exposure to DRSP in women with moderate liver impairment is approximately three times higher than the exposure in women with normal liver function. Beyaz has not been studied in women with severe hepatic impairment. [See Contraindications (4) and Warnings and Precautions (5.4).]

Drug Interactions

Consult the labeling of all concurrently used drugs to obtain further information about interactions with oral contraceptives or the potential for enzyme alterations.

Effects of Other Drugs on Combined Oral Contraceptives

Substances diminishing the efficacy of COCs: Drugs or herbal products that induce certain enzymes, including CYP3A4, may decrease the effectiveness of COCs or increase breakthrough bleeding.

Substances increasing the plasma concentrations of COCs: Co-administration of atorvastatin and certain COCs containing EE increase AUC values for EE by approximately 20%. Ascorbic acid and acetaminophen may increase plasma EE concentrations, possibly by inhibition of conjugation. In a clinical drug-drug interaction study conducted in 20 premenopausal women, co-administration of a DRSP (3 mg)/EE (0.02 mg) COC with the strong CYP3A4 inhibitor ketoconazole (200 mg twice daily) for 10 days increased the AUC(0-24h) of DRSP and EE by 2.68-fold (90% CI: 2.44, 2.95) and 1.40-fold (90% CI: 1.31, 1.49), respectively. The increases in Cmax were 1.97-fold (90% CI: 1.79, 2.17) and 1.39-fold (90% CI: 1.28, 1.52) for DRSP and EE, respectively. Although no clinically relevant effects on safety or laboratory parameters including serum potassium were observed, this study only assessed subjects for 10 days. The clinical impact for a patient taking a DRSP-containing COC concomitantly with chronic use of a CYP3A4/5 inhibitor is unknown [see Warnings and Precautions (5.2)].

HIV/HCV protease inhibitors and non-nucleoside reverse transcriptase inhibitors: Significant changes (increase or decrease) in the plasma concentrations of estrogen and progestin have been noted in some cases of co-administration with HIV/HCV protease inhibitors or with non-nucleoside reverse transcriptase inhibitors.

Antibiotics: There have been reports of pregnancy while taking hormonal contraceptives and antibiotics, but clinical pharmacokinetic studies have not shown consistent effects of antibiotics on plasma concentrations of synthetic steroids.

Effects of Combined Oral Contraceptives on Other Drugs

COCs containing EE may inhibit the metabolism of other compounds. COCs have been shown to significantly decrease plasma concentrations of lamotrigine, likely due to induction of lamotrigine glucuronidation. This may reduce seizure control; therefore, dosage adjustments of lamotrigine may be necessary. Consult the labeling of the concurrently-used drug to obtain further information about interactions with COCs or the potential for enzyme alterations.

In vitro, EE is a reversible inhibitor of CYP2C19, CYP1A1 and CYP1A2 as well as a mechanism-based inhibitor of CYP3A4/5, CYP2C8, and CYP2J2. Metabolism of DRSP and potential effects of DRSP on hepatic CYP enzymes have been investigated in in vitro and in vivo studies. In in vitro studies DRSP did not affect turnover of model substrates of CYP1A2 and CYP2D6, but had an inhibitory influence on the turnover of model substrates of CYP1A1, CYP2C9, CYP2C19, and CYP3A4, with CYP2C19 being the most sensitive enzyme. The potential effect of DRSP on CYP2C19 activity was investigated in a clinical pharmacokinetic study using omeprazole as a marker substrate. In the study with 24 postmenopausal women [including 12 women with homozygous (wild type) CYP2C19 genotype and 12 women with heterozygous CYP2C19 genotype] the daily oral administration of 3 mg DRSP for 14 days did not affect the oral clearance of omeprazole (40 mg, single oral dose) and the CYP2C19 product 5-hydroxy omeprazole. Furthermore, no significant effect of DRSP on the systemic clearance of the CYP3A4 product omeprazole sulfone was found. These results demonstrate that DRSP did not inhibit CYP2C19 and CYP3A4 in vivo.

Two additional clinical drug-drug interaction studies using simvastatin and midazolam as marker substrates for CYP3A4 were each performed in 24 healthy postmenopausal women. The results of these studies demonstrated that pharmacokinetics of the CYP3A4 substrates were not influenced by steady state DRSP concentrations achieved after administration of 3 mg DRSP/day.

Women on thyroid hormone replacement therapy may need increased doses of thyroid hormone because serum concentration of thyroid-binding globulin increases with use of COCs.

Interactions With Drugs That Have the Potential to Increase Serum Potassium Concentration:

There is a potential for an increase in serum potassium concentration in women taking Beyaz with other drugs that may increase serum potassium concentration [see Warnings and Precautions (5.2)].

A drug-drug interaction study of DRSP 3 mg/estradiol (E2) 1 mg versus placebo was performed in 24 mildly hypertensive postmenopausal women taking enalapril maleate 10 mg twice daily. Potassium concentrations were obtained every other day for a total of 2 weeks in all subjects. Mean serum potassium concentrations in the DRSP/E2 treatment group relative to baseline were 0.22 mEq/L higher than those in the placebo group. Serum potassium concentrations also were measured at multiple time points over 24 hours at baseline and on Day 14. On Day 14, the ratios for serum potassium Cmax and AUC in the DRSP/E2 group to those in the placebo group were 0.955 (90% CI: 0.914, 0.999) and 1.010 (90% CI: 0.944, 1.08), respectively. No patient in either treatment group developed hyperkalemia (serum potassium concentrations >5.5 mEq/L).

Effects of Folates on Other Drugs

There is a potential that folates such as folic acid and levomefolate calcium may modify the pharmacokinetics or pharmacodynamics of certain antifolate drugs (e.g., antiepileptics, methotrexate).

Effects of other Drugs on Folate

Several drugs (e.g., methotrexate, sulfasalazine, cholestyramine, antiepileptics) have been reported to reduce folate concentrations.

13 NONCLINICAL TOXICOLOGY

13.1 Carcinogenesis, Mutagenesis, Impairment of Fertility

In a 24 month oral carcinogenicity study in mice dosed with 10 mg/kg/day DRSP alone or 1 + 0.01, 3 + 0.03 and 10 + 0.1 mg/kg/day of DRSP and EE, 0.1 to 2 times the exposure (AUC of DRSP) of women taking a contraceptive dose, there was an increase in carcinomas of the harderian gland in the group that received the high dose of DRSP alone. In a similar study in rats given 10 mg/kg/day DRSP alone or 0.3 + 0.003, 3 + 0.03 and 10 + 0.1 mg/kg/day DRSP and EE, 0.8 to 10 times the exposure of women taking a contraceptive dose, there was an increased incidence of benign and total (benign and malignant) adrenal gland pheochromocytomas in the group receiving the high dose of DRSP. Mutagenesis studies for DRSP were conducted in vivo and in vitro and no evidence of mutagenic activity was observed. [see Warnings and Precautions (5.3), (5.4)].

Long-term animal studies have not been conducted to evaluate the carcinogenic potential of levomefolate. Mutagenesis studies for levomefolate were conducted in vitro and in vivo and no evidence of mutagenic activity was observed.

14 CLINICAL STUDIES

14.1 Oral Contraceptive Clinical Trial

In the primary contraceptive efficacy study of YAZ (3 mg DRSP/0.02 mg EE) of up to 1 year duration, 1,027 subjects were enrolled and completed 11,480 28-day cycles of use. The age range was 17 to 36 years. The racial demographic was: 87.8% Caucasian, 4.6% Hispanic, 4.3% Black, 1.2% Asian, and 2.1% other. Women with a BMI greater than 35 were excluded from the trial. The pregnancy rate (Pearl Index) was 1.41 (95% CI [0.73 – 2.47]) per 100 woman-years of use based on 12 pregnancies that occurred after the onset of treatment and within 14 days after the last dose of YAZ in women 35 years of age or younger during cycles in which no other form of contraception was used.

14.2 Premenstrual Dysphoric Disorder Clinical Trials

Two multicenter, double-blind, randomized, placebo-controlled studies were conducted to evaluate the effectiveness of YAZ in treating the symptoms of PMDD. Women aged 18-42 who met DSM-IV criteria for PMDD, confirmed by prospective daily ratings of their symptoms, were enrolled. Both studies measured the treatment effect of YAZ using the Daily Record of Severity of Problems scale, a patient-rated instrument that assesses the symptoms that constitute the DSM-IV diagnostic criteria. The primary study was a parallel group design that included 384 evaluable reproductive-aged women with PMDD who were randomly assigned to receive YAZ or placebo treatment for 3 menstrual cycles. The supportive study, a crossover design, was terminated prematurely prior to achieving recruitment goals due to enrollment difficulties. A total of 64 women of reproductive age with PMDD were treated initially with YAZ or placebo for up to 3 cycles followed by a washout cycle and then crossed over to the alternate medication for 3 cycles.

Efficacy was assessed in both studies by the change from baseline during treatment using a scoring system based on the first 21 items of the Daily Record of Severity of Problems. Each of the 21 items was rated on a scale from 1 (not at all) to 6 (extreme); thus a maximum score of 126 was possible. In both trials, women who received YAZ had statistically significantly greater improvement in their Daily Record of Severity of Problems scores. In the primary study, the average decrease (improvement) from baseline was 37.5 points in women taking YAZ, compared to 30.0 points in women taking placebo.

14.3 Acne Clinical Trials

In two multicenter, double-blind, randomized, placebo-controlled studies, 889 subjects, ages 14 to 45 years, with moderate acne received YAZ or placebo for six 28-day cycles. The primary efficacy endpoints were the percent change in inflammatory lesions, non-inflammatory lesions, total lesions, and the percentage of subjects with a "clear" or "almost clear" rating on the Investigator's Static Global Assessment (ISGA) scale on day 15 of cycle 6, as presented in Table 4:

Table 4: Efficacy Results for Acne Trials [Evaluated at day 15 of cycle 6, last observation carried forward for the Intent to treat population]
 | Study 1 |  | Study 2
 | YAZ | Placebo | YAZ | Placebo
 | N=228 | N=230 | N=218 | N=213
ISGA Success Rate | 35 (15%) | 10 (4%) | 46 (21%) | 19 (9%)
Inflammatory Lesions; Mean Baseline Count; Mean Absolute (%) Reduction | 33; 15 (48%) | 33; 11 (32%) | 32; 16 (51%) | 32; 11 (34%)
Non-inflammatory Lesions; Mean Baseline Count; Mean Absolute (%) Reduction | 47; 18 (39%) | 47; 10 (18%) | 44; 17 (42%) | 44; 11 (26%)
Total Lesions; Mean Baseline Count; Mean Absolute (%) Reduction | 80; 33 (42%) | 80; 21 (25%) | 76; 33 (46%) | 76; 22 (31%)

14.4 Folate Supplementation Clinical Trials

The development program for Beyaz consisted of two clinical trials.

One study was a multicenter, randomized, double-blind, active-controlled, parallel group US study. Plasma folate and red blood cell folate levels were investigated during a 24-week treatment with YAZ + 0.451 mg levomefolate calcium as compared to YAZ alone in a U.S. population with folate fortified food. A total of 379 healthy women between 18 and 40 years of age with no restrictions on folate supplementation received YAZ + levomefolate calcium (N= 285) or YAZ (N=94). The plasma and RBC folate concentrations at Week 24 were the co-primary endpoints. Figures 4 and 5 display the results for plasma and RBC folate, respectively, among evaluable subjects in each arm of the study.

Figure 4: US Study: Mean concentration-time curves (and SD) of plasma folates after daily oral administration of YAZ + levomefolate calcium and YAZ

Arithmetic mean values based on 4-weekly measurements are displayed with arithmetic standard deviations which are shown in only one direction to improve readability. Data are based on per protocol analysis populations. The SD bar shown represents a single SD.

Figure 5: US Study Mean concentration-time curves (and SD) of RBC folates after daily oral administration of YAZ + levomefolate calcium and YAZ

Arithmetic mean values based on 4-weekly measurements are displayed with arithmetic standard deviations which are shown in only one direction to improve readability. Data are based on per protocol analysis populations. The SD bar shown represents a single SD.

In the second study, the pharmacodynamic effect on plasma folate, RBC folate, and the profile of circulating folate metabolites was assessed during 24 weeks of treatment with 0.451 mg levomefolate calcium or with 0.4 mg folic acid (equimolar dose to 0.451 mg levomefolate calcium), both in combination with 3 mg DRSP/0.03 mg EE (Yasmin) followed by 20 weeks of open-label treatment with Yasmin only (elimination phase). One-hundred and seventy-two healthy women between 18 to 40 years of age from a German population without folate food fortification and without concomitant intake of folate supplements were randomized to one of the two treatments. Figures 6 and 7 display the results for plasma and RBC folate, respectively, among evaluable subjects in the levomefolate arm of the study.

Figure 6: German Study: Mean trough concentration-time curve (and SD) of plasma folates after daily oral administration of Yasmin + levomefolate calcium

Arithmetic mean values based on biweekly measurements are displayed with arithmetic standard deviations. In the treatment phase, women received Yasmin + levomefolate calcium; in the elimination phase, all women received Yasmin only. Data are based on per protocol analysis populations. The SD bar shown represents a single SD.

Figure 7: German Study: Mean concentration-time curves (and SD) of RBC folates after daily oral administration of Yasmin + levomefolate calcium

Arithmetic mean values based on biweekly measurements are displayed with arithmetic standard deviations. In the treatment phase, women received Yasmin + levomefolate calcium; in the elimination phase, all women received Yasmin only. Data are based on per protocol analysis populations. The SD bar shown represents a single SD.

The potential to reduce the incidence of neural tube defects (NTDs) with folate supplementation is well established based on a body of evidence derived from randomized, controlled trials, nonrandomized intervention trials, and observational studies using folic acid. Therefore, the Centers for Disease Control and Prevention (CDC) and the U.S. Preventive Services Task Force recommend that women of childbearing age consume supplemental folic acid in a dose of at least 0.4 mg (400 mcg) daily ^1,6.

15 REFERENCES

1. US Preventive Services Task Force. Folic Acid for the Prevention of Neural Tube Defects: US Preventive Services Task Force Recommendation Statement. Ann Intern Med 2009;150:626-631.

2. Seeger, J.D., Loughlin, J., Eng, P.M., Clifford, C.R., Cutone, J., and Walker, A.M. (2007). Risk of thromboembolism in women taking ethinylestradiol/drospirenone and other oral contraceptives. Obstet Gynecol 110, 587-593.

3. Dinger, J.C., Heinemann, L.A., and Kuhl-Habich, D. (2007). The safety of a drospirenone-containing oral contraceptive: final results from the European Active Surveillance Study on oral contraceptives based on 142,475 women-years of observation. Contraception 75, 344-354.

4. Combined hormonal contraceptives (CHCs) and the risk of cardiovascular endpoints. Sidney, S. (primary author) http://www.fda.gov/downloads/Drugs/DrugSafety/UCM277384.pdf, accessed Oct 27, 2011.

5. Lidegaard, O., Lokkegaard, E., Svendsen, A.L., and Agger, C. (2009). Hormonal contraception and risk of venous thromboembolism: national follow-up study. BMJ 339, b2890.

6. Lidegaard, O., Nielsen, L.H., Skovlund, C.W., Skjeldestad, F.E., and Lokkegaard, E. (2011). Risk of venous thromboembolism from use of oral contraceptives containing different progestogens and oestrogen doses: Danish cohort study, 2001-9. BMJ 343, d6423.

7. van Hylckama Vlieg, A., Helmerhorst, F.M., Vandenbroucke, J.P., Doggen, C.J., and Rosendaal, F.R. (2009). The venous thrombotic risk of oral contraceptives, effects of oestrogen dose and progestogen type: results of the MEGA case-control study. BMJ 339, b2921.

8. Dinger, J., Assmann, A., Mohner, S., and Minh, T.D. (2010). Risk of venous thromboembolism and the use of dienogest- and drospirenone-containing oral contraceptives: results from a German case-control study. J Fam Plann Reprod Health Care 36, 123-129.

9. Jick, S.S., and Hernandez, R.K. (2011). Risk of non-fatal venous thromboembolism in women using oral contraceptives containing drospirenone compared with women using oral contraceptives containing levonorgestrel: case-control study using United States claims data. BMJ 342, d2151.

10. Parkin, L., Sharples, K., Hernandez, R.K., and Jick, S.S. (2011). Risk of venous thromboembolism in users of oral contraceptives containing drospirenone or levonorgestrel: nested case-control study based on UK General Practice Research Database. BMJ 342, d2139.

11. Centers for Disease Control. Recommendations for the use of folic acid to reduce the number of cases of spina bifida and other neural tube defects. MMWR 1992;41(No. RR-14).

16 HOW SUPPLIED/STORAGE AND HANDLING

16.1 How Supplied

Beyaz (drospirenone/ethinyl estradiol/levomefolate calcium tablets and levomefolate calcium tablets) are available in packages of three blister packs (NDC 50419-407-03).

The film-coated tablets are rounded with biconvex faces, one side is embossed with a regular hexagon shape with Z+ or M+.

Each blister pack (28 film-coated tablets) contains in the following order:

- 24 round, biconvex, pink, film-coated tablets with embossed “Z+” in a regular hexagon on one side each containing 3 mg drospirenone, 0.02 mg ethinyl estradiol, and 0.451 mg levomefolate calcium
- 4 round, biconvex, light orange, film-coated tablets with embossed “M+” in a regular hexagon on one side each containing 0.451 mg levomefolate calcium

16.2 Storage

Store at 25°C (77°F); excursions permitted to 15-30°C (59-86°F) [see USP Controlled Room Temperature].

17 PATIENT COUNSELING INFORMATION

Advise the patient to read the FDA-approved patient labeling (Patient Information).

- Counsel patients that cigarette smoking increases the risk of serious cardiovascular events from COC use, and that women who are over 35 years old and smoke should not use COCs.
- Counsel patients that the increased risk of VTE compared to non-users of COCs is greatest after initially starting a COC or restarting (following a 4-week or greater pill-free interval) the same or a different COC.
- Counsel patients about the information regarding the risk of VTE with DRSP-containing COCs compared to COCs that contain levonorgestrel or some other progestins.
- Counsel patients that Beyaz does not protect against HIV-infection (AIDS) and other sexually transmitted diseases.
- Counsel patients on Warnings and Precautions associated with COCs.
- Counsel patients that Beyaz contains DRSP. Drospirenone may increase potassium. Patients should be advised to inform their healthcare provider if they have kidney, liver or adrenal disease because the use of Beyaz in the presence of these conditions could cause serious heart and health problems. They should also inform their healthcare provider if they are currently on daily, long-term treatment (NSAIDs, potassium-sparing diuretics, potassium supplementation, ACE inhibitors, angiotensin-II receptor antagonists, heparin or aldosterone antagonists) for a chronic condition or taking strong CYP3A4 inhibitors.
- Inform patients that Beyaz is not indicated during pregnancy. If pregnancy occurs during treatment with Beyaz, instruct the patient to stop further intake. However, women should be advised on the continued need of sufficient folate intake.
- Counsel patients to take one tablet daily by mouth at the same time every day. Instruct patients what to do in the event pills are missed.
- Counsel patients to use a back-up or alternative method of contraception when enzyme inducers are used with COCs.
- Counsel patients who are breastfeeding or who desire to breastfeed that COCs may reduce breast milk production. This is less likely to occur if breastfeeding is well established.
- Counsel any patient who starts COCs postpartum, and who has not yet had a period, to use an additional method of contraception until she has taken a pink tablet for 7 consecutive days.
- Counsel patients that amenorrhea may occur. Rule out pregnancy in the event of amenorrhea in two or more consecutive cycles.
- Counsel patients to report whether they are taking folate supplements. Beyaz contains the equivalent of 0.4 mg (400 mcg) of folic acid.
- Counsel patients to maintain folate supplementation if they discontinue Beyaz due to pregnancy.

FDA Approved Patient Labeling

Guide for Using Beyaz

WARNING TO WOMEN WHO SMOKE

Do not use Beyaz if you smoke cigarettes and are over 35 years old. Smoking increases your risk of serious cardiovascular side effects (heart and blood vessel problems) from birth control pills, including death from heart attack, blood clots or stroke. This risk increases with age and the number of cigarettes you smoke.

Birth control pills help to lower the chances of becoming pregnant when taken as directed. They do not protect against HIV infection (AIDS) and other sexually transmitted diseases.

What Is Beyaz?

Beyaz is a birth control pill. It contains two female hormones, a synthetic estrogen called ethinyl estradiol and a progestin called drospirenone. Beyaz also contains levomefolate calcium, which is a B vitamin.

The progestin drospirenone may increase potassium. Therefore, you should not take Beyaz if you have kidney, liver or adrenal disease because this could cause serious heart and health problems. Other drugs may also increase potassium. If you are currently on daily, long-term treatment for a chronic condition with any of the medications below, you should consult your healthcare provider about whether Beyaz is right for you, and during the first month that you take Beyaz, you should have a blood test to check your potassium level.

- NSAIDs (ibuprofen [Motrin, Advil], naproxen [Aleve and others] when taken long-term and daily for treatment of arthritis or other problems)
- Potassium-sparing diuretics (spironolactone and others)
- Potassium supplementation
- ACE inhibitors (Capoten, Vasotec, Zestril and others)
- Angiotensin-II receptor antagonists (Cozaar, Diovan, Avapro and others)
- Heparin
- Aldosterone antagonists

Beyaz may also be taken to treat premenstrual dysphoric disorder (PMDD) if you choose to use the Pill for birth control. Unless you have already decided to use the Pill for birth control, you should not start Beyaz to treat your PMDD because there are other medical therapies for PMDD that do not have the same risks as the Pill. PMDD is a mood disorder related to the menstrual cycle. PMDD significantly interferes with work or school, or with usual social activities and relationships with others. Symptoms include markedly depressed mood, anxiety or tension, mood swings, and persistent anger or irritability. Other features include decreased interest in usual activities, difficulty concentrating, lack of energy, change in appetite or sleep, and feeling out of control. Physical symptoms associated with PMDD may include breast tenderness, headache, joint and muscle pain, bloating and weight gain. These symptoms occur regularly before menstruation starts and go away within a few days following the start of the period. Diagnosis of PMDD should be made by healthcare providers.

You should only use Beyaz for treatment of PMDD if you:

- Have already decided to use oral contraceptives for birth control, and
- Have been diagnosed with PMDD by your healthcare provider.

Beyaz has not been shown to be effective for the treatment of premenstrual syndrome (PMS), a less serious set of symptoms occurring before menstruation. If you or your healthcare provider believe you have PMS, you should take Beyaz only if you want to prevent pregnancy; and not for the treatment of PMS.

Beyaz may also be taken to treat moderate acne if all of the following are true:

- Your healthcare provider says it is safe for you to use Beyaz.
- You are at least 14 years old.
- You have started having menstrual periods.
- You want to use a birth control pill to prevent pregnancy.

Beyaz may also be taken to provide folate supplementation in women who elect to use an oral contraceptive. It is recommended that women of reproductive age supplement their diet with 0.4 mg (400 mcg) of folic acid daily to lower their risk of having a pregnancy with a rare type of birth defect (known as a neural tube defect). The amount of folate contained in Beyaz supplements folate in the diet to lower this risk should you become pregnant while taking the drug or shortly after stopping it.

How Well Does Beyaz Work?

Your chance of getting pregnant depends on how well you follow the directions for taking your birth control pills. The better you follow the directions, the less chance you have of getting pregnant.

Based on the results of one clinical study, 1 to 2 women out of 100 women, may get pregnant during the first year they use Beyaz.

The following chart shows the chance of getting pregnant for women who use different methods of birth control. Each box on the chart contains a list of birth control methods that are similar in effectiveness. The most effective methods are at the top of the chart. The box on the bottom of the chart shows the chance of getting pregnant for women who do not use birth control and are trying to get pregnant.

How Do I Take Beyaz?

1. Be sure to read these directions before you start taking your pills or anytime you are not sure what to do.

2. The right way to take the pill is to take one pill every day at the same time in the order directed on the package. Preferably, take the pill after the evening meal or at bedtime, with some liquid, as needed. Beyaz can be taken without regard to meals.

If you miss pills you could get pregnant. This includes starting the pack late. The more pills you miss, the more likely you are to get pregnant. See "WHAT TO DO IF YOU MISS PILLS” below.

3. Many women have spotting or light bleeding at unexpected times, or may feel sick to their stomach during the first 1-3 packs of pills.

If you do have spotting or light bleeding or feel sick to your stomach, do not stop taking the pill. The problem will usually go away. If it does not go away, check with your healthcare provider.

4. Missing pills can also cause spotting or light bleeding, even when you make up these missed pills.

On the days you take two pills, to make up for missed pills, you could also feel a little sick to your stomach.

5. If you have vomiting (within 3 to 4 hours after you take your pill), you should follow the instructions for "WHAT TO DO IF YOU MISS PILLS." If you have diarrhea or if you take certain medicines, including some antibiotics and some herbal products such as St. John's Wort, your pills may not work as well.

Use a back-up method (such as condoms and spermicides) until you check with your healthcare provider.

6. If you have trouble remembering to take the pill, talk to your healthcare provider about how to make pill-taking easier or about using another method of birth control.

7. If you have any questions or are unsure about the information in this leaflet, call your healthcare provider.

Before You Start Taking Your Pills

1. Decide What Time of Day You Want to Take Your Pill

It is important to take Beyaz in the order directed on the package at the same time every day, preferably after the evening meal or at bedtime, with some liquid, as needed. Beyaz can be taken without regard to meals.

2. Look at Your Pill Pack—It has 28 Pills

The Beyaz-pill pack has 24 pink pills (with hormones and folate) to be taken for 24 days, followed by 4 light orange pills (without hormones, containing folate) to be taken for the next four days. It is important to take the light orange pills because they contain folate.

3. Also look for:

a) Where on the pack to start taking pills,

b) In what order to take the pills (follow the arrows)

4. Be sure you have ready at all times (a) another kind of birth control (such as condoms and spermicides) to use as a back-up in case you miss pills, and (b) an extra, full pill pack.

When To Start the First Pack of Pills

You have a choice for which day to start taking your first pack of pills. Decide with your healthcare provider which is the best day for you. Pick a time of day which will be easy to remember.

Day 1 Start:

1. Take the first pink pill of the pack during the first 24 hours of your period.

2. You will not need to use a back-up method of birth control, since you are starting the Pill at the beginning of your period. However, if you start Beyaz later than the first day of your period, you should use another method of birth control (such as a condom and spermicide) as a back-up method until you have taken 7 pink pills.

Sunday Start:

1. Take the first pink pill of the pack on the Sunday after your period starts, even if you are still bleeding. If your period begins on Sunday, start the pack that same day.

2. Use another method of birth control (such as a condom and spermicide) as a back-up method if you have sex anytime from the Sunday you start your first pack until the next Sunday (7 days). This also applies if you start Beyaz after having been pregnant, and you have not had a period since your pregnancy.

When You Switch From a Different Birth Control Pill

When switching from another birth control pill, Beyaz should be started on the same day that a new pack of the previous birth control pill would have been started.

When You Switch From Another Type of Birth Control Method

When switching from a transdermal patch or vaginal ring, Beyaz should be started when the next application would have been due. When switching from an injection, Beyaz should be started when the next dose would have been due. When switching from an intrauterine contraceptive or an implant, Beyaz should be started on the day of removal.

What to Do During the Month

1. Take one pill at the same time every day until the pack is empty.

Do not skip pills even if you are spotting or bleeding between monthly periods or feel sick to your stomach (nausea).

Do not skip pills even if you do not have sex very often.

2. When you finish a pack of pills, start the next pack on the day after your last light orange pill. It is important to take the light orange pills because they contain folate. Do not wait any days between packs.

What to Do if You Miss Pills

If you miss 1 pink pill in your pack:

1. Take it as soon as you remember. Take the next pill at your regular time. This means you may take two pills in one day.

2. You do not need to use a back-up birth control method if you have sex.

If you miss 2 pink pills in a row in Week 1 or Week 2 of your pack:

1. Take two pills on the day you remember and two pills the next day.

2. Then take one pill a day until you finish the pack.

3. You could become pregnant if you have sex in the 7 days after you restart your pills. You must use another birth control method (such as a condom and spermicide) as a back-up for those 7 days.

If you miss 2 pink pills in a row in Week 3 or Week 4 of your pack:

1. If you are a Day 1 Starter:

Throw out the rest of the pill pack and start a new pack that same day.

If you are a Sunday Starter:

Keep taking one pill every day until Sunday. On Sunday, throw out the rest of the pack and start a new pack of pills that same day.

2. You could become pregnant if you have sex in the 7 days after you restart your pills. You must use another birth control method (such as a condom and spermicide) as a back-up for those 7 days.

3. You may not have your period this month but this is expected. However, if you miss your period two months in a row, call your healthcare provider because you might be pregnant.

If you miss 3 or more pink pills in a row during any week:

1. If you are a Day 1 Starter:

Throw out the rest of the pill pack and start a new pack that same day.

If you are a Sunday Starter:

Keep taking 1 pill every day until Sunday. On Sunday, throw out the rest of the pack and start a new pack of pills that same day.

2. You could become pregnant if you have sex in the 7 days after you restart your pills. You must use another birth control method (such as condoms and spermicides) as a back-up for those 7 days.

3. You may not have your period this month but this is expected. However, if you miss your period two months in a row, call your healthcare provider because you might be pregnant.

If you miss any of the 4 light orange pills in Week 4:

Throw away the pills you missed.

Keep taking one pill each day until the pack is empty.

You do not need a back-up method.

Finally, if you are still not sure what to do about the pills you have missed:

Use a back-up method (such as condoms and spermicides) anytime you have sex.

Contact your healthcare provider and continue taking one active pink pill each day until otherwise directed.

WHO SHOULD NOT TAKE Beyaz?

Your healthcare provider will not give you Beyaz if you:

- Ever had blood clots in your legs (deep vein thrombosis), lungs (pulmonary embolism), or eyes (retinal thrombosis)
- Ever had a stroke
- Ever had a heart attack
- Have certain heart valve problems or heart rhythm abnormalities that can cause blood clots to form in the heart
- Have an inherited problem with your blood that makes it clot more than normal
- Have high blood pressure that medicine can't control
- Have diabetes with kidney, eye, nerve, or blood vessel damage
- Ever had certain kinds of severe migraine headaches with aura, numbness, weakness or changes in vision
- Ever had breast cancer which may be sensitive to female hormones
- Have liver disease, including liver tumors
- Take any Hepatitis C drug combination containing ombitasvir/paritaprevir/ritonavir, with or without dasabuvir. This may increase levels of the liver enzyme “alanine aminotransferase” (ALT) in the blood.
- Have kidney disease
- Have adrenal disease

Also, do not take birth control pills if you:

- Smoke and are over 35 years old
- Are or suspect you are pregnant

Birth control pills may not be a good choice for you if you have ever had jaundice (yellowing of the skin or eyes) caused by pregnancy (also called cholestasis of pregnancy).

Tell your healthcare provider if you have ever had any of the above conditions (your healthcare provider can recommend another method of birth control).

Tell your healthcare provider if you are already taking daily folate supplements.

What Else Should I Know about Taking Beyaz?

Birth control pills do not protect you against any sexually transmitted disease, including HIV, the virus that causes AIDS.

Do not skip any pills, even if you do not have sex often.

If you miss a period, you could be pregnant. However, some women miss periods or have light periods on birth control pills, even when they are not pregnant. Contact your healthcare provider for advice if you:

- Think you are pregnant
- Miss one period and have not taken your birth control pills every day
- Miss two periods in a row

Birth control pills should not be taken during pregnancy. However, birth control pills taken by accident during pregnancy are not known to cause birth defects.

You should stop Beyaz at least four weeks before you have major surgery and not restart it until at least two weeks after the surgery due to an increased risk of blood clots.

If you are breastfeeding, consider another birth control method until you are ready to stop breastfeeding. Birth control pills that contain estrogen, like Beyaz, may decrease the amount of milk you make. A small amount of the pill's hormones pass into breast milk.

Folates may make certain drugs, including some used for epilepsy, less effective, so talk to your healthcare provider about any medicines you take.

If you have vomiting or diarrhea, your birth control pills may not work as well. Use another birth control method, like condoms and a spermicide, until you check with your healthcare provider.

If you are scheduled for any laboratory tests, tell your doctor you are taking birth-control pills. Certain blood tests may be affected by birth-control pills.

Tell your healthcare provider about all the medicines you take, including prescription and over-the-counter medicines, vitamins and herbal supplements.

Beyaz may affect the way other medicines work, and other medicines may affect how well Beyaz works. Know the medicines you take.

Keep a list of them to show your healthcare provider and pharmacist when you get a new medicine.

What are the Most Serious Risks of Taking Birth Control Pills?

Like pregnancy, birth control pills increase the risk of serious blood clots (see following graph), especially in women who have other risk factors, such as smoking, obesity, or age greater than 35. This increased risk is highest when you first start taking birth control pills and when you restart the same or different birth control pills after not using them for a month or more. Women who use birth control pills with drospirenone (like Beyaz) may have a higher risk of getting a blood clot. Some studies reported that the risk of blood clots was higher for women who use birth control pills that contain drospirenone than for women who use birth control pills that do not contain drospirenone.

Talk with your healthcare provider about your risk of getting a blood clot before deciding which birth control pill is right for you.

It is possible to die or be permanently disabled from a problem caused by a blood clot, such as a heart attack or a stroke.

Some examples of serious clots are blood clots in the:

- Legs (deep vein thrombosis or DVT)
- Lungs (pulmonary embolus or PE)
- Eyes (loss of eyesight)
- Heart (heart attack)
- Brain (stroke)

To put the risk of developing a blood clot into perspective: If 10,000 women who are not pregnant and do not use birth control pills are followed for one year, between 1 and 5 of these women will develop a blood clot. The figure below shows the likelihood of developing a serious blood clot for women who are not pregnant and do not use birth control pills, for women who use birth control pills, for pregnant women, and for women in the first 12 weeks after delivering a baby.

Likelihood of Developing a Serious Blood Clot

A few women who take birth control pills may get:

- High blood pressure
- Gallbladder problems
- Rare cancerous or noncancerous liver tumors
All of these events are uncommon in healthy women.

Call your healthcare provider right away if you have:

- Persistent leg pain
- Sudden shortness of breath
- Sudden blindness, partial or complete
- Severe pain in your chest
- Sudden, severe headache unlike your usual headaches
- Weakness or numbness in an arm or leg, or trouble speaking
- Yellowing of the skin or eyeballs

What are the Common Side Effects of Birth Control Pills?

The most common side effects of birth control pills are:

- Spotting or bleeding between menstrual periods
- Nausea
- Breast tenderness
- Headache

These side effects are usually mild and usually disappear with time.

Less common side effects are:

- Acne
- Less sexual desire
- Bloating or fluid retention
- Blotchy darkening of the skin, especially on the face
- High blood sugar, especially in women who already have diabetes
- High fat (cholesterol; triglyceride) levels in the blood
- Depression, especially if you have had depression in the past. Call your healthcare provider immediately if you have any thoughts of harming yourself.
- Problems tolerating contact lenses
- Weight changes

This is not a complete list of possible side effects. Talk to your healthcare provider if you develop any side effects that concern you. You may report side effects to the FDA at 1-800-FDA-1088.

No serious problems have been reported from a birth control pill overdose, even when accidentally taken by children.

Do Birth Control Pills Cause Cancer?

It is not known if hormonal birth control pills cause breast cancer. Some studies, but not all, suggest that there could be a slight increase in the risk of breast cancer among current users with longer duration of use.

If you have breast cancer now, or have had it in the past, do not use hormonal birth control because some breast cancers are sensitive to hormones.

Women who use birth control pills may have a slightly higher chance of getting cervical cancer. However, this may be due to other reasons such as having more sexual partners.

What Should I Know about My Period when Taking Beyaz?

Irregular vaginal bleeding or spotting may occur while you are taking Beyaz. Irregular bleeding may vary from slight staining between menstrual periods to breakthrough bleeding, which is a flow much like a regular period. Irregular bleeding occurs most often during the first few months of oral contraceptive use, but may also occur after you have been taking the pill for some time. Such bleeding may be temporary and usually does not indicate any serious problems. It is important to continue taking your pills on schedule. If the bleeding occurs in more than one cycle, is unusually heavy, or lasts for more than a few days, call your healthcare provider.

Some women may not have a menstrual period but this should not be cause for alarm as long as you have taken the pills according to direction.

What if I Miss My Scheduled Period when Taking Beyaz?

It is not uncommon to miss your period. However, if you miss two periods in a row or miss one period when you have not taken your birth control pills according to directions, call your healthcare provider. Also notify your healthcare provider if you have symptoms of pregnancy such as morning sickness or unusual breast tenderness. It is important that your healthcare provider checks you to find out if you are pregnant. Stop taking Beyaz if you are pregnant.

What If I Want to Become Pregnant?

You may stop taking the pill whenever you wish. Consider a visit with your healthcare provider for a pre-pregnancy checkup before you stop taking the pill. See your health care provider about appropriate folate supplementation if you stop taking Beyaz, are pregnant, or plan on becoming pregnant.

General Advice about Beyaz

Your healthcare provider prescribed Beyaz for you. Please do not share Beyaz with anyone else. Keep Beyaz out of the reach of children.

If you have concerns or questions, ask your healthcare provider. You may also ask your healthcare provider for a more detailed label written for medical professionals.

Revised: 5/2023

Manufactured for:
Bayer HealthCare Pharmaceuticals Inc.
Whippany, NJ 07981

Manufactured in Germany

©2010 Bayer HealthCare Pharmaceuticals Inc. All Rights Reserved

Bayer HealthCare Pharmaceuticals Inc.

PACKAGE LABEL

Beyaz Trade Blisterpack

NDC 50419-407-01

1 Unit

Rx only

This product (like all oral contraceptives) is intended to prevent pregnancy. It does not protect against HIV infection (AIDS) and other sexually transmitted diseases.

BEYAZ
(drospirenone/ethinyl estradiol/ levomefolate calcium tablets and levomefolate calcium tablets)

www.beyaz.com

– 28 tablets

– oral